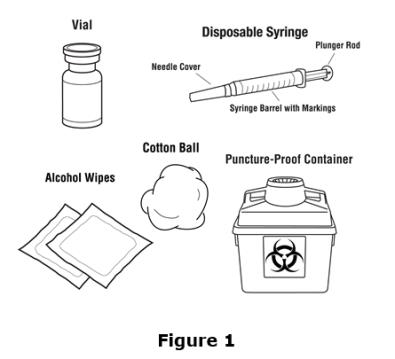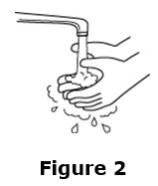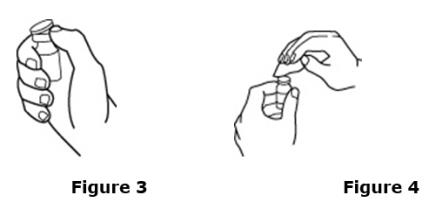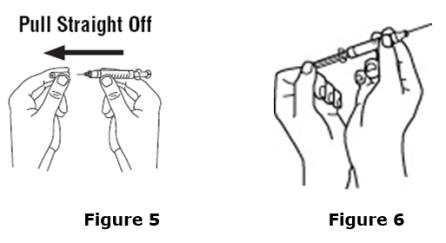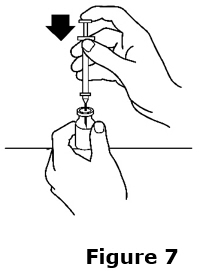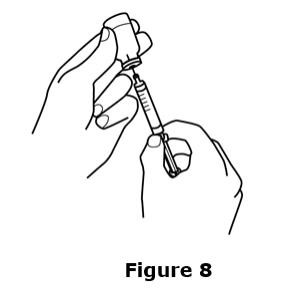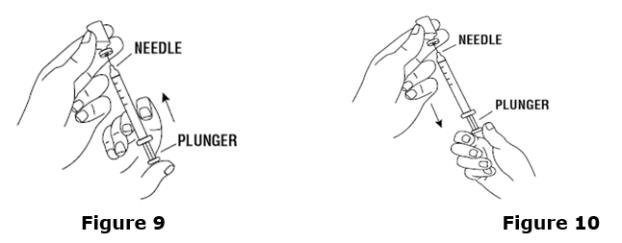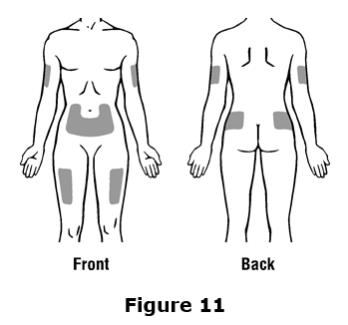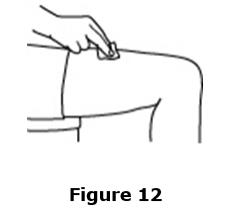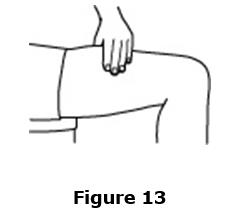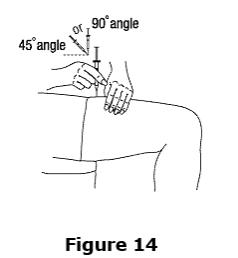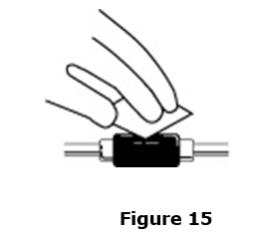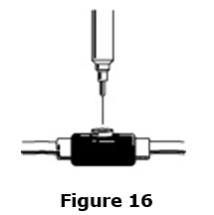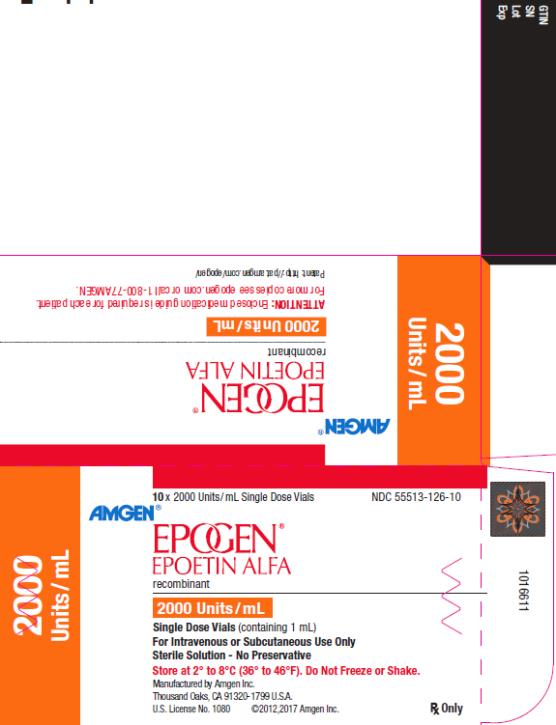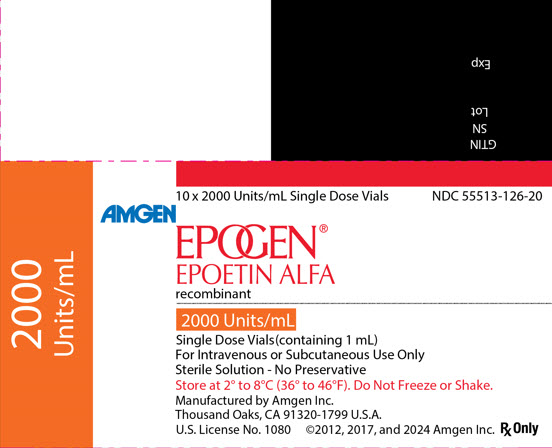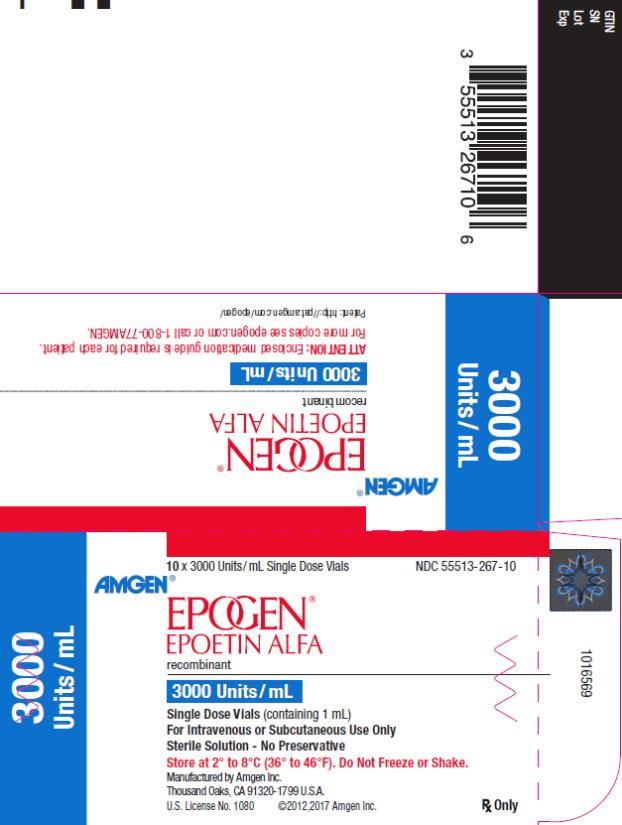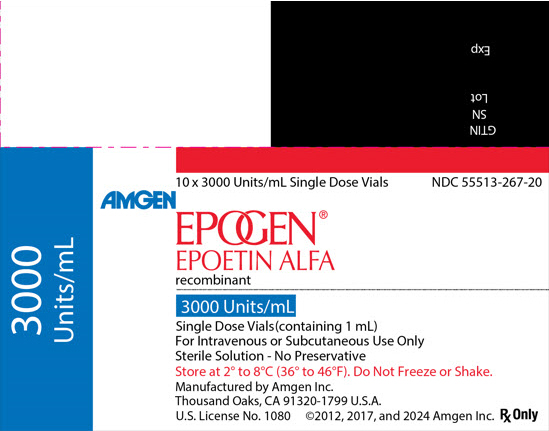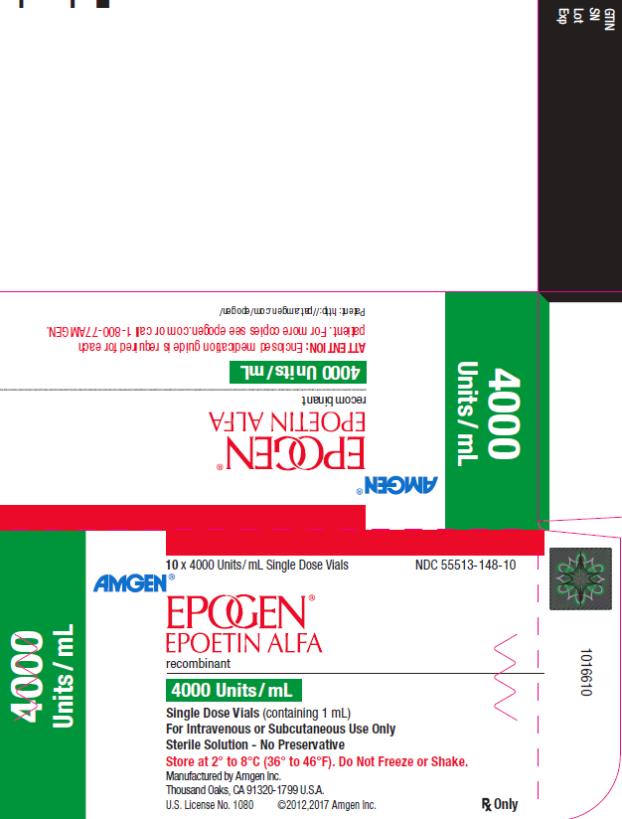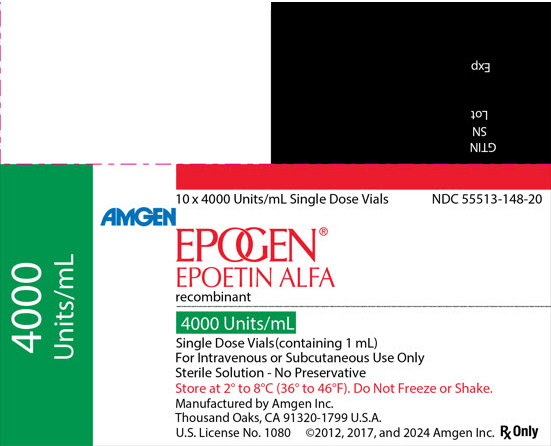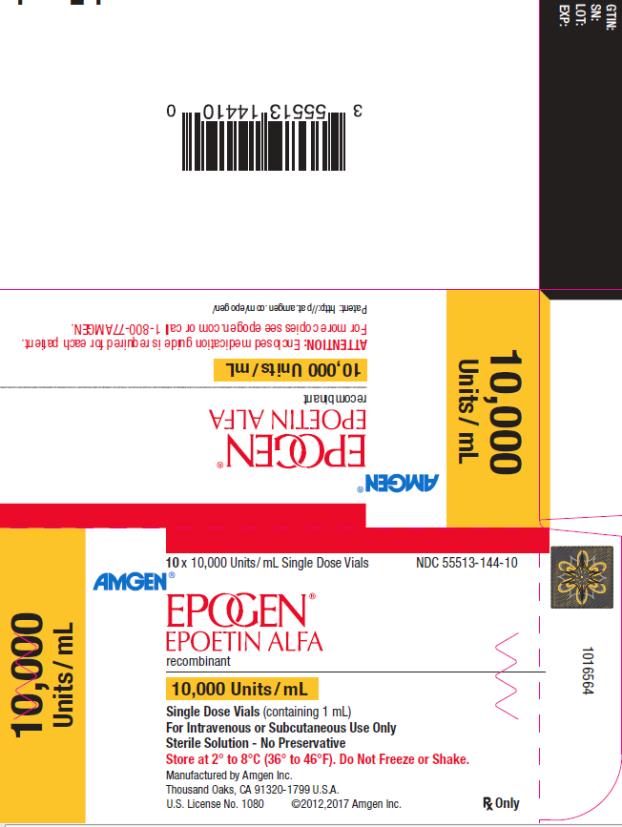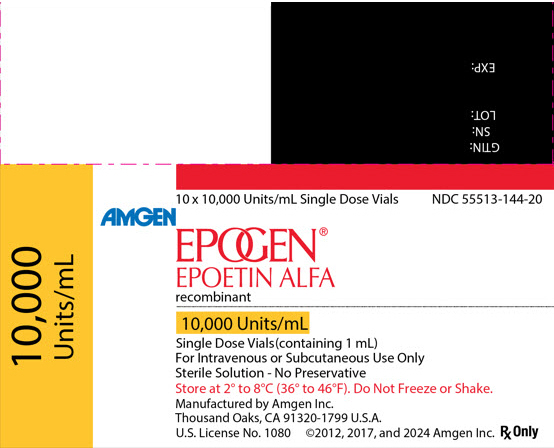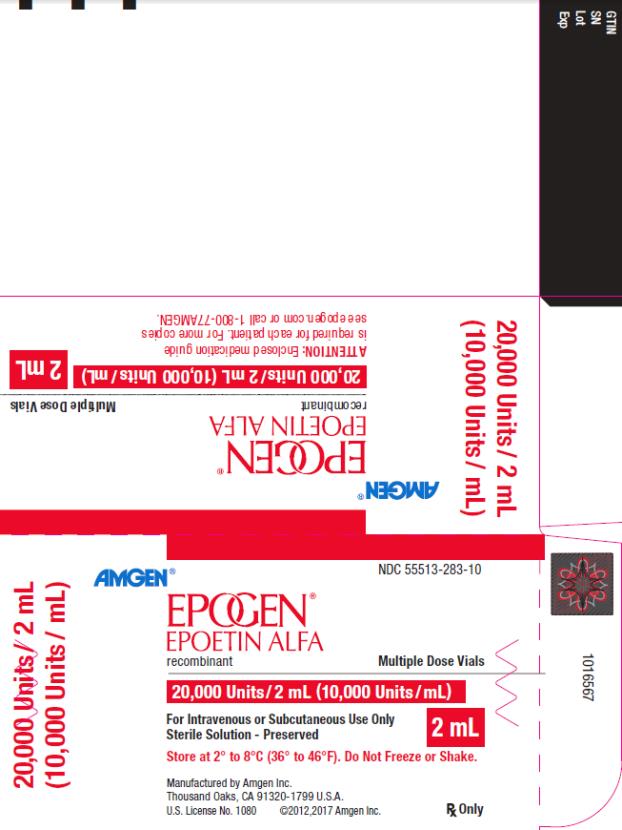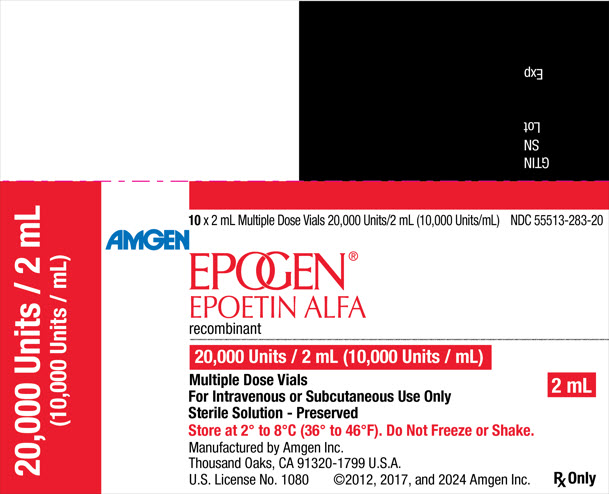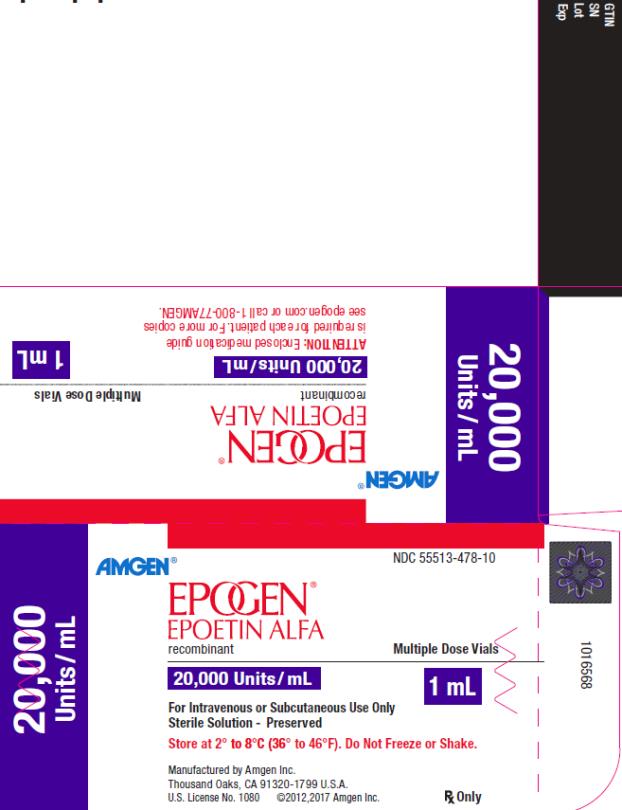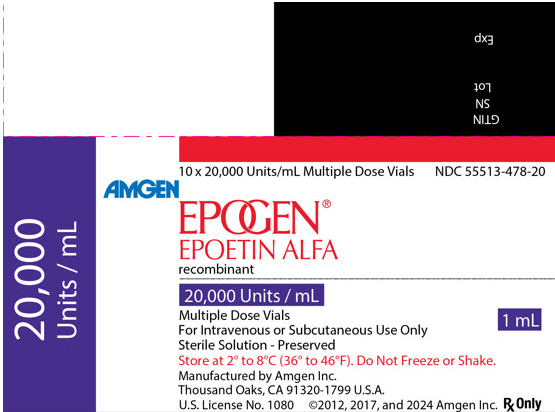 DRUG LABEL: EPOGEN
NDC: 55513-126 | Form: SOLUTION
Manufacturer: Amgen, Inc
Category: prescription | Type: HUMAN PRESCRIPTION DRUG LABEL
Date: 20251105

ACTIVE INGREDIENTS: EPOETIN 2000 [iU]/1 mL
INACTIVE INGREDIENTS: SODIUM CHLORIDE 5.9 mg/1 mL; SODIUM CITRATE, UNSPECIFIED FORM 5.8 mg/1 mL; CITRIC ACID MONOHYDRATE 0.06 mg/1 mL; ALBUMIN HUMAN 2.5 mg/1 mL

HIGHLIGHTS OF PRESCRIBING INFORMATION

These highlights do not include all the information needed to use EPOGEN safely and effectively. See full prescribing information for EPOGEN.
EPOGEN® (epoetin alfa) injection, for intravenous or subcutaneous use
Initial U.S. Approval: 1989

WARNING: ESAs INCREASE THE RISK OF DEATH, MYOCARDIAL INFARCTION, STROKE, VENOUS THROMBOEMBOLISM, THROMBOSIS OF VASCULAR ACCESS AND TUMOR PROGRESSION OR RECURRENCE

See full prescribing information for complete boxed warning.

Chronic Kidney Disease:

- In controlled trials, patients experienced greater risks for death, serious adverse cardiovascular reactions, and stroke when administered erythropoiesis-stimulating agents (ESAs) to target a hemoglobin level of greater than 11 g/dL (5.1).
- No trial has identified a hemoglobin target level, ESA dose, or dosing strategy that does not increase these risks (2.2).
- Use the lowest Epogen dose sufficient to reduce the need for red blood cell (RBC) transfusions (5.1).

Cancer:

- ESAs shortened overall survival and/or increased the risk of tumor progression or recurrence in clinical studies of patients with breast, non-small cell lung, head and neck, lymphoid, and cervical cancers (5.2).
- Use the lowest dose to avoid RBC transfusions (2.4).
- Use ESAs only for anemia from myelosuppressive chemotherapy (1.3).
- ESAs are not indicated for patients receiving myelosuppressive chemotherapy when the anticipated outcome is cure (1.5).
- Discontinue following the completion of a chemotherapy course (2.4).

Perisurgery:

- Due to increased risk of deep venous thrombosis (DVT), DVT prophylaxis is recommended (5.1).

1 INDICATIONS AND USAGE

Epogen is an erythropoiesis-stimulating agent (ESA) indicated for:

- Treatment of anemia due to:
  - Chronic Kidney Disease (CKD) in patients on dialysis and not on dialysis (1.1).
  - Zidovudine in patients with Human Immunodeficiency Virus (HIV) infection (1.2).
  - The effects of concomitant myelosuppressive chemotherapy, and upon initiation, there is a minimum of two additional months of planned chemotherapy (1.3).
- Reduction of allogeneic red blood cell (RBC) transfusions in patients undergoing elective, noncardiac, nonvascular surgery (1.4).

Limitations of Use

Epogen has not been shown to improve quality of life, fatigue, or patient well-being (1.5).

Epogen is not indicated for use:

- In patients with cancer receiving hormonal agents, biologic products, or radiotherapy, unless also receiving concomitant myelosuppressive chemotherapy (1.5).
- In patients with cancer receiving myelosuppressive chemotherapy when the anticipated outcome is cure (1.5).
- In patients with cancer receiving myelosuppressive chemotherapy in whom the anemia can be managed by transfusion (1.5).
- In patients scheduled for surgery who are willing to donate autologous blood (1.5).
- In patients undergoing cardiac or vascular surgery (1.5).
- As a substitute for RBC transfusions in patients who require immediate correction of anemia (1.5).

2 DOSAGE AND ADMINISTRATION

- Evaluate iron status before and during treatment and maintain iron repletion. Correct or exclude other causes of anemia before initiating treatment (2.1).
- In pregnant women, lactating women, neonates, infants: Use only single-dose vials (2.1).
- Patients with CKD: Initial dose: 50 to 100 Units/kg 3 times weekly (adults) and 50 Units/kg 3 times weekly (pediatric patients). Individualize maintenance dose. Intravenous route recommended for patients on hemodialysis (2.2).
- Patients on Zidovudine due to HIV infection: 100 Units/kg 3 times weekly (2.3).
- Patients with Cancer on Chemotherapy: 40,000 Units weekly or 150 Units/kg 3 times weekly (adults); 600 Units/kg intravenously weekly (pediatric patients ≥ 5 years) (2.4).
- Surgery Patients: 300 Units/kg per day daily for 15 days or 600 Units/kg weekly (2.5).

3 DOSAGE FORMS AND STRENGTHS

- Injection
  - 2,000 Units/mL, 3,000 Units/mL, 4,000 Units/mL, and 10,000 Units/mL in single-dose vials (3)
  - 20,000 Units/2 mL (10,000 Units/mL) and 20,000 Units/mL in multiple-dose vials containing benzyl alcohol (3)

4 CONTRAINDICATIONS

- Uncontrolled hypertension (4)
- Pure red cell aplasia (PRCA) that begins after treatment with Epogen or other erythropoietin protein drugs (4)
- Serious allergic reactions to Epogen (4)
- Use of the multiple-dose vials containing benzyl alcohol in neonates, infants, pregnant women, and lactating women (4)

5 WARNINGS AND PRECAUTIONS

- Increased Mortality, Myocardial Infarction, Stroke, and Thromboembolism: Using ESAs to target a hemoglobin level of greater than 11 g/dL increases the risk of serious adverse cardiovascular reactions and has not been shown to provide additional benefit (5.1 and 14.1). Use caution in patients with coexistent cardiovascular disease and stroke (5.1).
- Increased Mortality and/or Increased Risk of Tumor Progression or Recurrence in Patients with Cancer (5.2).
- Hypertension: Control hypertension prior to initiating and during treatment with Epogen (5.3).
- Seizures: Epogen increases the risk for seizures in patients with CKD (5.4). Increase monitoring of these patients for changes in seizure frequency or premonitory symptoms (5.4).
- PRCA: If severe anemia and low reticulocyte count develop during Epogen treatment, withhold Epogen and evaluate for PRCA (5.6).
- Serious Allergic Reactions: Discontinue Epogen and manage reactions (5.7).
- Severe Cutaneous Reactions: Discontinue Epogen (5.8).

6 ADVERSE REACTIONS

- Patients with CKD: Adverse reactions in ≥ 5% of Epogen-treated patients in clinical studies were hypertension, arthralgia, muscle spasm, pyrexia, dizziness, medical device malfunction, vascular occlusion, and upper respiratory tract infection (6.1).
- Patients on Zidovudine due to HIV infection: Adverse reactions in ≥ 5% of Epogen-treated patients in clinical studies were pyrexia, cough, rash, and injection site irritation (6.1).
- Patients with Cancer on Chemotherapy: Adverse reactions in ≥ 5% of Epogen-treated patients in clinical studies were nausea, vomiting, myalgia, arthralgia, stomatitis, cough, weight decrease, leukopenia, bone pain, rash, hyperglycemia, insomnia, headache, depression, dysphagia, hypokalemia, and thrombosis (6.1).
- Surgery Patients: Adverse reactions in ≥ 5% of Epogen-treated patients in clinical studies were nausea, vomiting, pruritus, headache, injection site pain, chills, deep vein thrombosis, cough, and hypertension (6.1).

To report SUSPECTED ADVERSE REACTIONS, contact Amgen Medical Information at 1-800-77-AMGEN (1-800-772-6436) or FDA at 1-800-FDA-1088 or www.fda.gov/medwatch.

FULL PRESCRIBING INFORMATION

WARNING: ESAs INCREASE THE RISK OF DEATH, MYOCARDIAL INFARCTION, STROKE, VENOUS THROMBOEMBOLISM, THROMBOSIS OF VASCULAR ACCESS AND TUMOR PROGRESSION OR RECURRENCE

Chronic Kidney Disease:

- In controlled trials, patients with chronic kidney disease (CKD) experienced greater risks for death, serious adverse cardiovascular reactions, and stroke when administered erythropoiesis-stimulating agents (ESAs) to target a hemoglobin level of greater than 11 g/dL [see Warnings and Precautions (5.1)].
- No trial has identified a hemoglobin target level, ESA dose, or dosing strategy that does not increase these risks [see Dosage and Administration (2.2)].
- Use the lowest Epogen dose sufficient to reduce the need for red blood cell (RBC) transfusions [see Warnings and Precautions (5.1)].

Cancer:

- ESAs shortened overall survival and/or increased the risk of tumor progression or recurrence in clinical studies of patients with breast, non-small cell lung, head and neck, lymphoid, and cervical cancers [see Warnings and Precautions (5.2)].
- To decrease these risks, as well as the risk of serious cardiovascular and thromboembolic reactions, use the lowest dose needed to avoid RBC transfusions [see Dosage and Administration (2.4)].
- Use ESAs only for anemia from myelosuppressive chemotherapy [see Indications and Usage (1.3)].
- ESAs are not indicated for patients receiving myelosuppressive chemotherapy when the anticipated outcome is cure [see Indications and Usage (1.5)].
- Discontinue following the completion of a chemotherapy course [see Dosage and Administration (2.4)].

Perisurgery:

- Due to increased risk of Deep Venous Thrombosis (DVT), DVT prophylaxis is recommended [see Dosage and Administration (2.5), Warnings and Precautions (5.1)].

1 INDICATIONS AND USAGE

1.1 Anemia Due to Chronic Kidney Disease

Epogen is indicated for the treatment of anemia due to chronic kidney disease (CKD), including patients on dialysis and not on dialysis to decrease the need for red blood cell (RBC) transfusion.

1.2 Anemia Due to Zidovudine in Patients with HIV Infection

Epogen is indicated for the treatment of anemia due to zidovudine administered at ≤ 4200 mg/week in patients with HIV infection with endogenous serum erythropoietin levels of ≤ 500 mUnits/mL.

1.3 Anemia Due to Chemotherapy in Patients with Cancer

Epogen is indicated for the treatment of anemia in patients with non-myeloid malignancies where anemia is due to the effect of concomitant myelosuppressive chemotherapy, and upon initiation, there is a minimum of two additional months of planned chemotherapy.

1.4 Reduction of Allogeneic Red Blood Cell Transfusions in Patients Undergoing Elective, Noncardiac, Nonvascular Surgery

Epogen is indicated to reduce the need for allogeneic RBC transfusions among patients with perioperative hemoglobin > 10 to ≤ 13 g/dL who are at high risk for perioperative blood loss from elective, noncardiac, nonvascular surgery. Epogen is not indicated for patients who are willing to donate autologous blood pre-operatively.

1.5 Limitations of Use

Epogen has not been shown to improve quality of life, fatigue, or patient well-being.

Epogen is not indicated for use:

- In patients with cancer receiving hormonal agents, biologic products, or radiotherapy, unless also receiving concomitant myelosuppressive chemotherapy.
- In patients with cancer receiving myelosuppressive chemotherapy when the anticipated outcome is cure.
- In patients with cancer receiving myelosuppressive chemotherapy in whom the anemia can be managed by transfusion.
- In patients scheduled for surgery who are willing to donate autologous blood.
- In patients undergoing cardiac or vascular surgery.
- As a substitute for RBC transfusions in patients who require immediate correction of anemia.

2 DOSAGE AND ADMINISTRATION

2.1 Important Dosing Information

Evaluation of Iron Stores and Nutritional Factors

Evaluate the iron status in all patients before and during treatment. Administer supplemental iron therapy when serum ferritin is less than 100 mcg/L or when serum transferrin saturation is less than 20%. The majority of patients with CKD will require supplemental iron during the course of ESA therapy.

Monitoring of Response to Therapy

Correct or exclude other causes of anemia (e.g., vitamin deficiency, metabolic or chronic inflammatory conditions, bleeding, etc.) before initiating Epogen. Following initiation of therapy and after each dose adjustment, monitor hemoglobin weekly until the hemoglobin level is stable and sufficient to minimize the need for RBC transfusion.

Selection of Formulation

In pregnant women, lactating women, neonates, and infants use only single-dose vials (the benzyl alcohol-free formulation) [see Contraindications (4) and Use in Specific Populations (8.1, 8.2, and 8.4)].

2.2 Patients with Chronic Kidney Disease

In controlled trials, patients experienced greater risks for death, serious adverse cardiovascular reactions, and stroke when administered ESAs to target a hemoglobin level of greater than 11 g/dL. No trial has identified a hemoglobin target level, ESA dose, or dosing strategy that does not increase these risks. Individualize dosing and use the lowest dose of Epogen sufficient to reduce the need for RBC transfusions [see Warnings and Precautions (5.1)]. Physicians and patients should weigh the possible benefits of decreasing transfusions against the increased risks of death and other serious cardiovascular adverse reactions [see Boxed Warning and Clinical Studies (14)].

For all patients with CKD:

When initiating or adjusting therapy, monitor hemoglobin levels at least weekly until stable, then monitor at least monthly. When adjusting therapy consider hemoglobin rate of rise, rate of decline, ESA responsiveness and hemoglobin variability. A single hemoglobin excursion may not require a dosing change.

- Do not increase the dose more frequently than once every 4 weeks. Decreases in dose can occur more frequently. Avoid frequent dose adjustments.
- If the hemoglobin rises rapidly (e.g., more than 1 g/dL in any 2-week period), reduce the dose of Epogen by 25% or more as needed to reduce rapid responses.
- For patients who do not respond adequately, if the hemoglobin has not increased by more than 1 g/dL after 4 weeks of therapy, increase the dose by 25%.
- For patients who do not respond adequately over a 12-week escalation period, increasing the Epogen dose further is unlikely to improve response and may increase risks. Use the lowest dose that will maintain a hemoglobin level sufficient to reduce the need for RBC transfusions. Evaluate other causes of anemia. Discontinue Epogen if responsiveness does not improve.

For adult patients with CKD on dialysis:

- Initiate Epogen treatment when the hemoglobin level is less than 10 g/dL.
- If the hemoglobin level approaches or exceeds 11 g/dL, reduce or interrupt the dose of Epogen.
- The recommended starting dose for adult patients is 50 to 100 Units/kg 3 times weekly intravenously or subcutaneously. The intravenous route is recommended for patients on hemodialysis.

For adult patients with CKD not on dialysis:

- Consider initiating Epogen treatment only when the hemoglobin level is less than 10 g/dL and the following considerations apply:
  - The rate of hemoglobin decline indicates the likelihood of requiring a RBC transfusion and,
  - Reducing the risk of alloimmunization and/or other RBC transfusion-related risks is a goal
- If the hemoglobin level exceeds 10 g/dL, reduce or interrupt the dose of Epogen, and use the lowest dose of Epogen sufficient to reduce the need for RBC transfusions.
- The recommended starting dose for adult patients is 50 to 100 Units/kg 3 times weekly intravenously or subcutaneously.

For pediatric patients with CKD:

• Initiate Epogen treatment only when the hemoglobin level is less than 10 g/dL.

• If the hemoglobin level approaches or exceeds 12 g/dL, reduce or interrupt the dose of Epogen.

• The recommended starting dose for pediatric patients (ages 1 month or older) is 50 Units/kg 3 times weekly intravenously or subcutaneously.

When treating patients who have chronic kidney disease and cancer, physicians should refer to Warnings and Precautions (5.1 and 5.2).

2.3 Zidovudine-treated Patients with HIV Infection

Starting Dose

The recommended starting dose in adults is 100 Units/kg as an intravenous or subcutaneous injection 3 times per week.

Dose Adjustment

- If hemoglobin does not increase after 8 weeks of therapy, increase Epogen dose by approximately 50 to 100 Units/kg at 4- to 8-week intervals until hemoglobin reaches a level needed to avoid RBC transfusions or 300 Units/kg.
- Withhold Epogen if hemoglobin exceeds 12 g/dL. Resume therapy at a dose 25% below the previous dose when hemoglobin declines to less than 11 g/dL.

Discontinue Epogen if an increase in hemoglobin is not achieved at a dose of 300 Units/kg for 8 weeks.

2.4 Patients on Cancer Chemotherapy

Initiate Epogen in patients on cancer chemotherapy only if the hemoglobin is less than 10 g/dL, and if there is a minimum of two additional months of planned chemotherapy.

Use the lowest dose of Epogen necessary to avoid RBC transfusions.

Recommended Starting Dose

Adults:

- 150 Units/kg subcutaneously 3 times per week until completion of a chemotherapy course or
- 40,000 Units subcutaneously weekly until completion of a chemotherapy course.

Pediatric Patients (5 to 18 years):

- 600 Units/kg intravenously weekly until completion of a chemotherapy course.

Dose Reduction

Reduce dose by 25% if:

- Hemoglobin increases greater than 1 g/dL in any 2-week period or
- Hemoglobin reaches a level needed to avoid RBC transfusion.

Withhold dose if hemoglobin exceeds a level needed to avoid RBC transfusion. Reinitiate at a dose 25% below the previous dose when hemoglobin approaches a level where RBC transfusions may be required.

Dose Increase

After the initial 4 weeks of Epogen therapy, if hemoglobin increases by less than 1 g/dL and remains below 10 g/dL, increase dose to:

- 300 Units/kg three times per week in adults or
- 60,000 Units weekly in adults
- 900 Units/kg (maximum 60,000 Units) weekly in pediatric patients

After 8 weeks of therapy, if there is no response as measured by hemoglobin levels or if RBC transfusions are still required, discontinue Epogen.

2.5 Surgery Patients

The recommended Epogen regimens are:

- 300 Units/kg per day subcutaneously for 15 days total: administered daily for 10 days before surgery, on the day of surgery, and for 4 days after surgery.
- 600 Units/kg subcutaneously in 4 doses administered 21, 14, and 7 days before surgery and on the day of surgery.

Deep venous thrombosis prophylaxis is recommended during Epogen therapy [see Warnings and Precautions (5.1)].

2.6 Preparation and Administration

- Do not shake. Do not use Epogen that has been shaken or frozen.
- Protect vials from light.
- Parenteral drug products should be inspected visually for particulate matter and discoloration prior to administration. Do not use any vials exhibiting particulate matter or discoloration.
- Discard unused portions of Epogen in preservative-free vials. Do not re-enter preservative-free vials.
- Store unused portions of Epogen in multiple-dose vials at 36°F to 46°F (2°C to 8°C). Discard 21 days after initial entry.
- Do not dilute. Do not mix with other drug solutions except for admixing as described below:

Preservative-free Epogen from single-dose vials may be admixed in a syringe with bacteriostatic 0.9% sodium chloride injection, USP, with benzyl alcohol 0.9% (bacteriostatic saline) in a 1:1 ratio using aseptic technique at the time of administration. Do not mix Epogen with bacteriostatic saline when administering to pregnant women, lactating women, neonates, and infants [see Use in Specific Populations (8.1, 8.2, 8.4)].

3 DOSAGE FORMS AND STRENGTHS

Injection:

- 2,000 Units/mL, 3,000 Units/mL, 4,000 Units/mL, and 10,000 Units/mL of Epogen as a clear and colorless liquid in single-dose vials.
- 20,000 Units/2 mL (10,000 Units/mL) and 20,000 Units/mL of Epogen as a clear and colorless liquid in multiple-dose vials (contains benzyl alcohol).

4 CONTRAINDICATIONS

Epogen is contraindicated in patients with:

- Uncontrolled hypertension [see Warnings and Precautions (5.3)]
- Pure red cell aplasia (PRCA) that begins after treatment with Epogen or other erythropoietin protein drugs [see Warnings and Precautions (5.6)]
- Serious allergic reactions to Epogen [see Warnings and Precautions (5.7)]

Epogen from multiple-dose vials contains benzyl alcohol and is contraindicated in:

- Neonates, infants, pregnant women, and lactating women [see Warnings and Precautions (5.9), Use in Specific Populations (8.1, 8.2, 8.4)].

5 WARNINGS AND PRECAUTIONS

5.1 Increased Mortality, Myocardial Infarction, Stroke, and Thromboembolism

- In controlled clinical trials of patients with CKD comparing higher hemoglobin targets (13 – 14 g/dL) to lower targets (9 - 11.3 g/dL), Epogen and other ESAs increased the risk of death, myocardial infarction, stroke, congestive heart failure, thrombosis of hemodialysis vascular access, and other thromboembolic events in the higher target groups.
- Using ESAs to target a hemoglobin level of greater than 11 g/dL increases the risk of serious adverse cardiovascular reactions and has not been shown to provide additional benefit [see Clinical Studies (14.1)]. Use caution in patients with coexistent cardiovascular disease and stroke [see Dosage and Administration (2.2)]. Patients with CKD and an insufficient hemoglobin response to ESA therapy may be at even greater risk for cardiovascular reactions and mortality than other patients. A rate of hemoglobin rise of greater than 1 g/dL over 2 weeks may contribute to these risks.
- In controlled clinical trials of patients with cancer, Epogen and other ESAs increased the risks for death and serious adverse cardiovascular reactions. These adverse reactions included myocardial infarction and stroke.
- In controlled clinical trials, ESAs increased the risk of death in patients undergoing coronary artery bypass graft surgery (CABG) and the risk of deep venous thrombosis (DVT) in patients undergoing orthopedic procedures.

The design and overall results of the 3 large trials comparing higher and lower hemoglobin targets are shown in Table 1.

Table 1. Randomized Controlled Trials Showing Adverse Cardiovascular Outcomes in Patients with CKD
 | Normal Hematocrit Study (NHS) (N = 1265) | CHOIR (N = 1432) | TREAT (N = 4038)
Time Period of Trial | 1993 to 1996 | 2003 to 2006 | 2004 to 2009
Population | CKD patients on hemodialysis with coexisting CHF or CAD, hematocrit 30 ± 3% on epoetin alfa | CKD patients not on dialysis with hemoglobin < 11 g/dL not previously administered epoetin alfa | CKD patients not on dialysis with type II diabetes, hemoglobin ≤ 11 g/dL
Hemoglobin Target; Higher vs. Lower (g/dL) | 14.0 vs. 10.0 | 13.5 vs. 11.3 | 13.0 vs. ≥ 9.0
Median (Q1, Q3) Achieved Hemoglobin level (g/dL) | 12.6 (11.6, 13.3) vs. 10.3 (10.0, 10.7) | 13.0 (12.2, 13.4) vs. 11.4 (11.1, 11.6) | 12.5 (12.0, 12.8) vs. 10.6 (9.9, 11.3)
Primary Endpoint | All-cause mortality or non-fatal MI | All-cause mortality, MI, hospitalization for CHF, or stroke | All-cause mortality, MI, myocardial ischemia, heart failure, and stroke
Hazard Ratio or Relative Risk (95% CI) | 1.28 (1.06 - 1.56) | 1.34 (1.03 - 1.74) | 1.05 (0.94 - 1.17)
Adverse Outcome for Higher Target Group | All-cause mortality | All-cause mortality | Stroke
Hazard Ratio or Relative Risk (95% CI) | 1.27 (1.04 - 1.54) | 1.48 (0.97 - 2.27) | 1.92 (1.38 - 2.68)

Patients with Chronic Kidney Disease

Normal Hematocrit Study (NHS): A prospective, randomized, open-label study of 1265 patients with chronic kidney disease on dialysis with documented evidence of congestive heart failure or ischemic heart disease was designed to test the hypothesis that a higher target hematocrit (Hct) would result in improved outcomes compared with a lower target Hct. In this study, patients were randomized to epoetin alfa treatment targeted to a maintenance hemoglobin of either 14 ± 1 g/dL or 10 ± 1 g/dL. The trial was terminated early with adverse safety findings of higher mortality in the high hematocrit target group. Higher mortality (35% vs. 29%) was observed for the patients randomized to a target hemoglobin of 14 g/dL than for the patients randomized to a target hemoglobin of 10 g/dL. For all-cause mortality, the HR = 1.27; 95% CI (1.04, 1.54); p = 0.018. The incidence of nonfatal myocardial infarction, vascular access thrombosis, and other thrombotic events was also higher in the group randomized to a target hemoglobin of 14 g/dL.

CHOIR: A randomized, prospective trial, 1432 patients with anemia due to CKD who were not undergoing dialysis and who had not previously received epoetin alfa therapy were randomized to epoetin alfa treatment targeting a maintenance hemoglobin concentration of either 13.5 g/dL or 11.3 g/dL. The trial was terminated early with adverse safety findings. A major cardiovascular event (death, myocardial infarction, stroke, or hospitalization for congestive heart failure) occurred in 125 of the 715 patients (18%) in the higher hemoglobin group compared to 97 of the 717 patients (14%) in the lower hemoglobin group [hazard ratio (HR) 1.34, 95% CI: 1.03, 1.74; p = 0.03].

TREAT: A randomized, double-blind, placebo-controlled, prospective trial of 4038 patients with: CKD not on dialysis (eGFR of 20 – 60 mL/min), anemia (hemoglobin levels ≤ 11 g/dL), and type 2 diabetes mellitus, patients were randomized to receive either darbepoetin alfa treatment or a matching placebo. Placebo group patients also received darbepoetin alfa when their hemoglobin levels were below 9 g/dL. The trial objectives were to demonstrate the benefit of darbepoetin alfa treatment of the anemia to a target hemoglobin level of 13 g/dL, when compared to a "placebo" group, by reducing the occurrence of either of two primary endpoints: (1) a composite cardiovascular endpoint of all-cause mortality or a specified cardiovascular event (myocardial ischemia, CHF, MI, and CVA) or (2) a composite renal endpoint of all-cause mortality or progression to end stage renal disease. The overall risks for each of the two primary endpoints (the cardiovascular composite and the renal composite) were not reduced with darbepoetin alfa treatment (see Table 1), but the risk of stroke was increased nearly two-fold in the darbepoetin alfa-treated group versus the placebo group: annualized stroke rate 2.1% vs. 1.1%, respectively, HR 1.92; 95% CI: 1.38, 2.68; p < 0.001. The relative risk of stroke was particularly high in patients with a prior stroke: annualized stroke rate 5.2% in the darbepoetin alfa-treated group and 1.9% in the placebo group, HR 3.07; 95% CI: 1.44, 6.54. Also, among darbepoetin alfa-treated subjects with a past history of cancer, there were more deaths due to all causes and more deaths adjudicated as due to cancer, in comparison with the control group.

Patients with Cancer

An increased incidence of thromboembolic reactions, some serious and life-threatening, occurred in patients with cancer treated with ESAs.

In a randomized, placebo-controlled study (Study 2 in Table 2 [see Warnings and Precautions (5.2)]) of 939 women with metastatic breast cancer receiving chemotherapy, patients received either weekly epoetin alfa or placebo for up to a year. This study was designed to show that survival was superior when epoetin alfa was administered to prevent anemia (maintain hemoglobin levels between 12 and 14 g/dL or hematocrit between 36% and 42%). This study was terminated prematurely when interim results demonstrated a higher mortality at 4 months (8.7% vs. 3.4%) and a higher rate of fatal thrombotic reactions (1.1% vs. 0.2%) in the first 4 months of the study among patients treated with epoetin alfa. Based on Kaplan-Meier estimates, at the time of study termination, the 12-month survival was lower in the epoetin alfa group than in the placebo group (70% vs. 76%; HR 1.37, 95% CI: 1.07, 1.75; p = 0.012).

Patients Having Surgery

An increased incidence of deep venous thrombosis (DVT) in patients receiving epoetin alfa undergoing surgical orthopedic procedures was demonstrated [see Adverse Reactions (6.1)]. In a randomized, controlled study, 680 adult patients, not receiving prophylactic anticoagulation and undergoing spinal surgery, were randomized to 4 doses of 600 Units/kg epoetin alfa (7, 14, and 21 days before surgery, and the day of surgery) and standard of care (SOC) treatment (n = 340) or to SOC treatment alone (n = 340). A higher incidence of DVTs, determined by either color flow duplex imaging or by clinical symptoms, was observed in the epoetin alfa group (16 [4.7%] patients) compared with the SOC group (7 [2.1%] patients). In addition to the 23 patients with DVTs included in the primary analysis, 19 [2.8%] patients (n = 680) experienced 1 other thrombovascular event (TVE) each (12 [3.5%] in the epoetin alfa group and 7 [2.1%] in the SOC group). Deep venous thrombosis prophylaxis is strongly recommended when ESAs are used for the reduction of allogeneic RBC transfusions in surgical patients [see Dosage and Administration (2.5)].

Increased mortality was observed in a randomized, placebo-controlled study of Epogen in adult patients who were undergoing CABG surgery (7 deaths in 126 patients randomized to Epogen versus no deaths among 56 patients receiving placebo). Four of these deaths occurred during the period of study drug administration and all 4 deaths were associated with thrombotic events.

5.2 Increased Mortality and/or Increased Risk of Tumor Progression or Recurrence in Patients with Cancer

ESAs resulted in decreased locoregional control/progression-free survival (PFS) and/or overall survival (OS) (see Table 2).

Adverse effects on PFS and/or OS were observed in studies of patients receiving chemotherapy for breast cancer (Studies 1, 2, and 4), lymphoid malignancy (Study 3), and cervical cancer (Study 5); in patients with advanced head and neck cancer receiving radiation therapy (Studies 6 and 7); and in patients with non-small cell lung cancer or various malignancies who were not receiving chemotherapy or radiotherapy (Studies 8 and 9).

Table 2. Randomized, Controlled Studies with Decreased Survival and/or Decreased Locoregional Control

Study/Tumor/(n) | Hemoglobin Target | Achieved Hemoglobin (Median; Q1, Q3 [Q1 = 25th percentile; Q3 = 75th percentile]) | Primary Efficacy Outcome | Adverse Outcome for ESA- containing Arm
Chemotherapy
Study 1 Metastatic breast cancer (n = 2098) | ≤ 12 g/dL [This study did not include a defined hemoglobin target. Doses were titrated to achieve and maintain the lowest hemoglobin level sufficient to avoid transfusion and not to exceed 12 g/dL.] | 11.6 g/dL; 10.7, 12.1 g/dL | Progression-free survival (PFS) | Decreased progression-free and overall survival
Study 2 Metastatic breast cancer (n = 939) | 12-14 g/dL | 12.9 g/dL; 12.2, 13.3 g/dL | 12-month overall survival | Decreased 12- month survival
Study 3 Lymphoid malignancy (n = 344) | 13-15 g/dL (M) 13-14 g/dL (F) | 11 g/dL; 9.8, 12.1 g/dL | Proportion of patients achieving a hemoglobin response | Decreased overall survival
Study 4 Early breast cancer (n = 733) | 12.5-13 g/dL | 13.1 g/dL; 12.5, 13.7 g/dL | Relapse-free and overall survival | Decreased 3-year relapse-free and overall survival
Study 5 Cervical cancer (n = 114) | 12-14 g/dL | 12.7 g/dL; 12.1, 13.3 g/dL | Progression-free and overall survival and locoregional control | Decreased 3-year progression-free and overall survival and locoregional control
Radiotherapy Alone
Study 6 Head and neck cancer (n = 351) | ≥ 15 g/dL (M) ≥ 14 g/dL (F) | Not available | Locoregional progression-free survival | Decreased 5-year locoregional progression-free and overall survival
Study 7 Head and neck cancer (n = 522) | 14-15.5 g/dL | Not available | Locoregional disease control | Decreased locoregional disease control
No Chemotherapy or Radiotherapy
Study 8 Non-small cell lung cancer (n = 70) | 12-14 g/dL | Not available | Quality of life | Decreased overall survival
Study 9 Non-myeloid malignancy (n = 989) | 12-13 g/dL | 10.6 g/dL; 9.4, 11.8 g/dL | RBC transfusions | Decreased overall survival

Decreased Overall Survival

Study 2 was described in the previous section [see Warnings and Precautions (5.1)]. Mortality at 4 months (8.7% vs. 3.4%) was significantly higher in the epoetin alfa arm. The most common investigator-attributed cause of death within the first 4 months was disease progression; 28 of 41 deaths in the epoetin alfa arm and 13 of 16 deaths in the placebo arm were attributed to disease progression. Investigator-assessed time to tumor progression was not different between the 2 groups. Survival at 12 months was significantly lower in the epoetin alfa arm (70% vs. 76%; HR 1.37, 95% CI: 1.07, 1.75; p = 0.012).

Study 3 was a randomized, double-blind study (darbepoetin alfa vs. placebo) conducted in 344 anemic patients with lymphoid malignancy receiving chemotherapy. With a median follow-up of 29 months, overall mortality rates were significantly higher among patients randomized to darbepoetin alfa as compared to placebo (HR 1.36, 95% CI: 1.02, 1.82).

Study 8 was a multicenter, randomized, double-blind study (epoetin alfa vs. placebo) in which patients with advanced non-small cell lung cancer receiving only palliative radiotherapy or no active therapy were treated with epoetin alfa to achieve and maintain hemoglobin levels between 12 and 14 g/dL. Following an interim analysis of 70 patients (planned accrual 300 patients), a significant difference in survival in favor of the patients in the placebo arm of the study was observed (median survival 63 vs. 129 days; HR 1.84; p = 0.04).

Study 9 was a randomized, double-blind study (darbepoetin alfa vs. placebo) in 989 anemic patients with active malignant disease, neither receiving nor planning to receive chemotherapy or radiation therapy. There was no evidence of a statistically significant reduction in proportion of patients receiving RBC transfusions. The median survival was shorter in the darbepoetin alfa treatment group than in the placebo group (8 months vs. 10.8 months; HR 1.30, 95% CI: 1.07, 1.57).

Decreased Progression-free Survival and Overall Survival

Study 1 was a randomized, open-label, multicenter study in 2,098 anemic women with metastatic breast cancer, who received first line or second line chemotherapy. This was a non-inferiority study designed to rule out a 15% risk increase in tumor progression or death of epoetin alfa plus standard of care (SOC) as compared with SOC alone. At the time of clinical data cutoff, the median progression-free survival (PFS) per investigator assessment of disease progression was 7.4 months in each arm (HR 1.09, 95% CI: 0.99, 1.20), indicating the study objective was not met. There were more deaths from disease progression in the epoetin alfa plus SOC arm (59% vs. 56%) and more thrombotic vascular events in the epoetin alfa plus SOC arm (3% vs. 1%). At the final analysis, 1653 deaths were reported (79.8% subjects in the epoetin alfa plus SOC group and 77.8% subjects in the SOC group. Median overall survival in the epoetin alfa plus SOC group was 17.8 months compared with 18.0 months in the SOC alone group (HR 1.07, 95% CI: 0.97, 1.18).

Study 4 was a randomized, open-label, controlled, factorial design study in which darbepoetin alfa was administered to prevent anemia in 733 women receiving neo-adjuvant breast cancer treatment. A final analysis was performed after a median follow-up of approximately 3 years. The 3-year survival rate was lower (86% vs. 90%; HR 1.42, 95% CI: 0.93, 2.18) and the 3-year relapse-free survival rate was lower (72% vs. 78%; HR 1.33, 95% CI: 0.99, 1.79) in the darbepoetin alfa-treated arm compared to the control arm.

Study 5 was a randomized, open-label, controlled study that enrolled 114 of a planned 460 cervical cancer patients receiving chemotherapy and radiotherapy. Patients were randomized to receive epoetin alfa to maintain hemoglobin between 12 and 14 g/dL or to RBC transfusion support as needed. The study was terminated prematurely due to an increase in thromboembolic adverse reactions in epoetin alfa-treated patients compared to control (19% vs. 9%). Both local recurrence (21% vs. 20%) and distant recurrence (12% vs. 7%) were more frequent in epoetin alfa-treated patients compared to control. Progression-free survival at 3 years was lower in the epoetin alfa-treated group compared to control (59% vs. 62%; HR 1.06, 95% CI: 0.58, 1.91). Overall survival at 3 years was lower in the epoetin alfa-treated group compared to control (61% vs. 71%; HR 1.28, 95% CI: 0.68, 2.42).

Study 6 was a randomized, placebo-controlled study in 351 head and neck cancer patients where epoetin beta or placebo was administered to achieve target hemoglobins ≥ 14 and ≥ 15 g/dL for women and men, respectively. Locoregional progression-free survival was significantly shorter in patients receiving epoetin beta (HR 1.62, 95% CI: 1.22, 2.14; p = 0.0008) with medians of 406 days and 745 days in the epoetin beta and placebo arms, respectively. Overall survival was significantly shorter in patients receiving epoetin beta (HR 1.39, 95% CI: 1.05, 1.84; p = 0.02).

Decreased Locoregional Control

Study 7 was a randomized, open-label, controlled study conducted in 522 patients with primary squamous cell carcinoma of the head and neck receiving radiation therapy alone (no chemotherapy) who were randomized to receive darbepoetin alfa to maintain hemoglobin levels of 14 to 15.5 g/dL or no darbepoetin alfa. An interim analysis performed on 484 patients demonstrated that locoregional control at 5 years was significantly shorter in patients receiving darbepoetin alfa (RR 1.44, 95% CI: 1.06, 1.96; p = 0.02). Overall survival was shorter in patients receiving darbepoetin alfa (RR 1.28, 95% CI: 0.98, 1.68; p = 0.08).

5.3 Hypertension

Epogen is contraindicated in patients with uncontrolled hypertension. Following initiation and titration of Epogen, approximately 25% of patients on dialysis required initiation of or increases in antihypertensive therapy; hypertensive encephalopathy and seizures have been reported in patients with CKD receiving Epogen.

Appropriately control hypertension prior to initiation of and during treatment with Epogen. Reduce or withhold Epogen if blood pressure becomes difficult to control. Advise patients of the importance of compliance with antihypertensive therapy and dietary restrictions [see Patient Counseling Information (17)].

5.4 Seizures

Epogen increases the risk of seizures in patients with CKD. During the first several months following initiation of Epogen, monitor patients closely for premonitory neurologic symptoms. Advise patients to contact their healthcare practitioner for new-onset seizures, premonitory symptoms or change in seizure frequency.

5.5 Lack or Loss of Hemoglobin Response to Epogen

For lack or loss of hemoglobin response to Epogen, initiate a search for causative factors (e.g., iron deficiency, infection, inflammation, bleeding). If typical causes of lack or loss of hemoglobin response are excluded, evaluate for PRCA [see Warnings and Precautions (5.6)]. In the absence of PRCA, follow dosing recommendations for management of patients with an insufficient hemoglobin response to Epogen therapy [see Dosage and Administration (2.2)].

5.6 Pure Red Cell Aplasia

Cases of PRCA and of severe anemia, with or without other cytopenias that arise following the development of neutralizing antibodies to erythropoietin have been reported in patients treated with Epogen. This has been reported predominantly in patients with CKD receiving ESAs by subcutaneous administration. PRCA has also been reported in patients receiving ESAs for anemia related to hepatitis C treatment (an indication for which Epogen is not approved).

If severe anemia and low reticulocyte count develop during treatment with Epogen, withhold Epogen and evaluate patients for neutralizing antibodies to erythropoietin. Contact Amgen (1-800-77-AMGEN) to perform assays for binding and neutralizing antibodies. Permanently discontinue Epogen in patients who develop PRCA following treatment with Epogen or other erythropoietin protein drugs. Do not switch patients to other ESAs.

5.7 Serious Allergic Reactions

Serious allergic reactions, including anaphylactic reactions, angioedema, bronchospasm, skin rash, and urticaria may occur with Epogen. Immediately and permanently discontinue Epogen and administer appropriate therapy if a serious allergic or anaphylactic reaction occurs.

5.8 Severe Cutaneous Reactions

Blistering and skin exfoliation reactions including Erythema multiforme and Stevens-Johnson Syndrome (SJS)/Toxic Epidermal Necrolysis (TEN), have been reported in patients treated with ESAs (including Epogen) in the postmarketing setting. Discontinue Epogen therapy immediately if a severe cutaneous reaction, such as SJS/TEN, is suspected.

5.9 Risk of Serious Adverse Reactions Due to Benzyl Alcohol Preservative

Epogen from multiple-dose vials contains benzyl alcohol and is contraindicated for use in neonates, infants, pregnant women, and lactating women [see Contraindications (4)]. In addition, do not mix Epogen with bacteriostatic saline (which also contains benzyl alcohol) when administering Epogen to these patient populations [see Dosage and Administration (2)].

Serious and fatal reactions including “gasping syndrome” can occur in neonates and infants treated with benzyl alcohol-preserved drugs, including Epogen multiple-dose vials. The “gasping syndrome” is characterized by central nervous system (CNS) depression, metabolic acidosis, and gasping respirations. There is a potential for similar risks to fetuses and infants exposed to benzyl alcohol in utero or in breast-fed milk, respectively. Epogen multiple-dose vials contain 11 mg of benzyl alcohol per mL. The minimum amount of benzyl alcohol at which serious adverse reactions may occur is not known [see Use in Specific Populations (8.1, 8.2, and 8.4)].

5.10 Risk of Infectious Diseases Due to Albumin (Human) Content

Epogen contains albumin, a derivative of human blood [see Description (11)]. Based on effective donor screening and product manufacturing processes, it carries an extremely remote risk for transmission of viral diseases. A theoretical risk for transmission of Creutzfeldt-Jakob disease (CJD) also is considered extremely remote. No cases of transmission of viral diseases or CJD have ever been identified for albumin.

5.11 Dialysis Management

Patients may require adjustments in their dialysis prescriptions after initiation of Epogen. Patients receiving Epogen may require increased anticoagulation with heparin to prevent clotting of the extracorporeal circuit during hemodialysis.

6 ADVERSE REACTIONS

The following serious adverse reactions are discussed in greater detail in other sections of the label:

- Increased Mortality, Myocardial Infarction, Stroke, and Thromboembolism [see Warnings and Precautions (5.1)]
- Increased Mortality and/or Increased Risk of Tumor Progression or Recurrence in Patients with Cancer [see Warnings and Precautions (5.2)]
- Hypertension [see Warnings and Precautions (5.3)]
- Seizures [see Warnings and Precautions (5.4)]
- PRCA [see Warnings and Precautions (5.6)]
- Serious Allergic Reactions [see Warnings and Precautions (5.7)]
- Severe Cutaneous Reactions [see Warnings and Precautions (5.8)]

6.1 Clinical Trial Experience

Because clinical trials are conducted under widely varying conditions, adverse reaction rates observed in the clinical trials of a drug cannot be directly compared to rates in the clinical trials of other drugs and may not reflect the rates observed in practice.

Patients with Chronic Kidney Disease

Adult Patients

Three double-blind, placebo-controlled studies, including 244 patients with CKD on dialysis, were used to identify the adverse reactions to Epogen. In these studies, the mean age of patients was 48 years (range: 20 to 80 years). One hundred and thirty-three (55%) patients were men. The racial distribution was as follows: 177 (73%) patients were white, 48 (20%) patients were black, 4 (2%) patients were Asian, 12 (5%) patients were other, and racial information was missing for 3 (1%) patients.

Two double-blind, placebo-controlled studies, including 210 patients with CKD not on dialysis, were used to identify the adverse reactions to Epogen. In these studies, the mean age of patients was 57 years (range: 24 to 79 years). One hundred and twenty-one (58%) patients were men. The racial distribution was as follows: 164 (78%) patients were white, 38 (18%) patients were black, 3 (1%) patients were Asian, 3 (1%) patients were other, and racial information was missing for 2 (1%) patients.

The adverse reactions with a reported incidence of ≥ 5% in Epogen-treated patients and that occurred at a ≥ 1% higher frequency than in placebo-treated patients are shown in the table below:

Table 3. Adverse Reactions in Patients with CKD on Dialysis
Adverse Reaction | Epogen-treated Patients (n = 148) | Placebo-treated Patients (n = 96)
Hypertension | 27.7% | 12.5%
Arthralgia | 16.2% | 3.1%
Muscle spasm | 7.4% | 6.3%
Pyrexia | 10.1% | 8.3%
Dizziness | 9.5% | 8.3%
Medical Device Malfunction (artificial kidney clotting during dialysis) | 8.1% | 4.2%
Vascular Occlusion (vascular access thrombosis) | 8.1% | 2.1%
Upper respiratory tract infection | 6.8% | 5.2%

An additional serious adverse reaction that occurred in less than 5% of epoetin alfa-treated dialysis patients and greater than placebo was thrombosis (2.7% Epogen and 1% placebo) [see Warnings and Precautions (5.1)].

The adverse reactions with a reported incidence of ≥ 5% in Epogen-treated patients and that occurred at a ≥ 1% higher frequency than in placebo-treated patients are shown in the table below:

Table 4. Adverse Reactions in Patients with CKD Not on Dialysis
Adverse Reaction | Epogen-treated Patients (n = 131) | Placebo-treated Patients (n = 79)
Hypertension | 13.7% | 10.1%
Arthralgia | 12.2% | 7.6%

Additional serious adverse reactions that occurred in less than 5% of epoetin alfa-treated patients not on dialysis and greater than placebo were erythema (0.8% Epogen and 0% placebo) and myocardial infarction (0.8% Epogen and 0% placebo) [see Warnings and Precautions (5.1)].

Pediatric Patients

In pediatric patients with CKD on dialysis, the pattern of adverse reactions was similar to that found in adults.

Zidovudine-treated Patients with HIV Infection

A total of 297 zidovudine-treated patients with HIV infection were studied in 4 placebo-controlled studies. A total of 144 (48%) patients were randomly assigned to receive Epogen and 153 (52%) patients were randomly assigned to receive placebo. Epogen was administered at doses between 100 and 200 Units/kg 3 times weekly subcutaneously for up to 12 weeks.

For the combined Epogen treatment groups, a total of 141 (98%) men and 3 (2%) women between the ages of 24 and 64 years were enrolled. The racial distribution of the combined Epogen treatment groups was as follows: 129 (90%) white, 8 (6%) black, 1 (1%) Asian, and 6 (4%) other.

In double-blind, placebo-controlled studies of 3 months duration involving approximately 300 zidovudine-treated patients with HIV infection, adverse reactions with an incidence of ≥ 1% in patients treated with Epogen were:

Table 5. Adverse Reactions in Zidovudine-treated Patients with HIV infection
Adverse Reaction | Epogen (n = 144) | Placebo (n = 153)
Pyrexia | 42% | 34%
Cough | 26% | 14%
Rash | 19% | 7%
Injection site irritation | 7% | 4%
Urticaria | 3% | 1%
Respiratory tract congestion | 1% | Not reported
Pulmonary embolism | 1% | Not reported

Patients with Cancer on Chemotherapy

The data below were obtained in Study C1, a 16-week, double-blind, placebo-controlled study that enrolled 344 patients with anemia secondary to chemotherapy. There were 333 patients who were evaluable for safety; 168 of 174 patients (97%) randomized to Epogen received at least 1 dose of study drug, and 165 of 170 patients (97%) randomized to placebo received at least 1 placebo dose. For the once weekly Epogen-treatment group, a total of 76 men (45%) and 92 women (55%) between the ages of 20 and 88 years were treated. The racial distribution of the Epogen-treatment group was 158 white (94%) and 10 black (6%). Epogen was administered once weekly for an average of 13 weeks at a dose of 20,000 to 60,000 IU subcutaneously (mean weekly dose was 49,000 IU).

The adverse reactions with a reported incidence of ≥ 5% in Epogen-treated patients that occurred at a higher frequency than in placebo-treated patients are shown in the table below:

Table 6. Adverse Reactions in Patients with Cancer
Adverse Reaction | Epogen (n = 168) | Placebo (n = 165)
Nausea | 35% | 30%
Vomiting | 20% | 16%
Myalgia | 10% | 5%
Arthralgia | 10% | 6%
Stomatitis | 10% | 8%
Cough | 9% | 7%
Weight decrease | 9% | 5%
Leukopenia | 8% | 7%
Bone pain | 7% | 4%
Rash | 7% | 5%
Hyperglycemia | 6% | 4%
Insomnia | 6% | 2%
Headache | 5% | 4%
Depression | 5% | 4%
Dysphagia | 5% | 2%
Hypokalemia | 5% | 3%
Thrombosis | 5% | 3%

Surgery Patients

Four hundred sixty-one patients undergoing major orthopedic surgery were studied in a placebo-controlled study (S1) and a comparative dosing study (2 dosing regimens, S2). A total of 358 patients were randomly assigned to receive Epogen and 103 (22%) patients were randomly assigned to receive placebo. Epogen was administered daily at a dose of 100 to 300 IU/kg subcutaneously for 15 days or at 600 IU/kg once weekly for 4 weeks.

For the combined Epogen treatment groups, a total of 90 (25%) men and 268 (75%) women between the ages of 29 and 89 years were enrolled. The racial distribution of the combined Epogen treatment groups was as follows: 288 (80%) white, 64 (18%) black, 1 (< 1%) Asian, and 5 (1%) other.

The adverse reactions with a reported incidence of ≥ 1% in Epogen-treated patients that occurred at a higher frequency than in placebo-treated patients are shown in the table below:

Table 7. Adverse Reactions in Surgery Patients
 | Study S1 |  |  | Study S2
Adverse Reaction | Epogen 300 U/kg (n = 112) [Study included patients undergoing orthopedic surgery treated with Epogen or placebo for 15 days.] | Epogen 100 U/kg (n = 101) | Placebo (n = 103) | Epogen 600 U/kg × 4 weeks (n = 73) [Study included patients undergoing orthopedic surgery treated with Epogen 600 U/kg weekly for 4 weeks or 300 U/kg daily for 15 days.] | Epogen 300 U/kg × 15 days (n = 72)
Nausea | 47% | 43% | 45% | 45% | 56%
Vomiting | 21% | 12% | 14% | 19% | 28%
Pruritus | 16% | 16% | 14% | 12% | 21%
Headache | 13% | 11% | 9% | 10% | 18%
Injection site pain | 13% | 9% | 8% | 12% | 11%
Chills | 7% | 4% | 1% | 1% | 0%
Deep vein thrombosis | 6% | 3% | 3% | 0% [DVTs were determined by clinical symptoms.] | 0%
Cough | 5% | 4% | 0% | 4% | 4%
Hypertension | 5% | 3% | 5% | 5% | 6%
Rash | 2% | 2% | 1% | 3% | 3%
Edema | 1% | 2% | 2% | 1% | 3%

6.2 Postmarketing Experience

The following adverse reactions have been identified during post-approval use of Epogen.

Because these reactions are reported voluntarily from a population of uncertain size, it is not always possible to reliably estimate their frequency or establish a causal relationship to drug exposure.

- Seizures [see Warnings and Precautions (5.4)]
- PRCA [see Warnings and Precautions (5.6)]
- Serious Allergic Reactions [see Warnings and Precautions (5.7)]
- Injection Site Reactions, including irritation and pain
- Porphyria
- Severe Cutaneous Reactions [see Warnings and Precautions (5.8)]

6.3 Immunogenicity

As with all therapeutic proteins, there is a potential for immunogenicity. The detection of antibody formation is highly dependent on the sensitivity and specificity of the assay. Additionally, the observed incidence of antibody (including neutralizing antibody) positivity in an assay may be influenced by several factors, including assay methodology, sample handling, timing of sample collection, concomitant medications, and underlying disease. For these reasons, comparison of the incidence of antibodies to epoetin alfa with the incidence of antibodies to other products may be misleading.

Neutralizing antibodies to epoetin alfa that cross-react with endogenous erythropoietin and other ESAs can result in PRCA or severe anemia (with or without other cytopenias) [see Warnings and Precautions (5.6)].

8 USE IN SPECIFIC POPULATIONS

8.1 Pregnancy

Risk Summary

Epogen from multiple-dose vials contains benzyl alcohol and is contraindicated in pregnant women [see Contraindications (4)]. When therapy with Epogen is needed during pregnancy, use a benzyl alcohol-free formulation (i.e., single-dose vial). Do not mix Epogen with bacteriostatic saline when administering to pregnant women because it contains benzyl alcohol (see Clinical Considerations) [see Dosage and Administration (2.1)].

The limited available data on Epogen use in pregnant women are insufficient to determine a drug-associated risk of adverse developmental outcomes. In animal reproductive and developmental toxicity studies, adverse fetal effects including embryo-fetal death, skeletal anomalies, and growth defects occurred when pregnant rats received epoetin alfa at doses approximating the clinical recommended starting doses (see Data). Consider the benefits and risks of Epogen single-dose vials for the mother and possible risks to the fetus when prescribing Epogen to a pregnant woman.

The estimated background risk of major birth defects and miscarriage for the indicated population is unknown. All pregnancies have a background risk of birth defect, loss, or other adverse outcomes. In the U.S. general population, the estimated background risks of major birth defects and miscarriage in clinically recognized pregnancies is 2-4% and 15-20%, respectively.

Clinical Considerations

Fetal/Neonatal Adverse Reactions

The multiple-dose vials of Epogen contain benzyl alcohol. The preservative benzyl alcohol has been associated with serious adverse reactions and death when administered intravenously to neonates and infants [see Warnings and Precautions (5.9), Use in Specific Populations (8.4)]. There is a potential for similar risks to fetuses exposed to benzyl alcohol in utero.

Data

Human Data

There are reports of pregnant women with anemia alone or anemia associated with severe renal disease and other hematologic disorders who received Epogen. Polyhydramnios and intrauterine growth restriction were reported in women with chronic renal disease, which is associated with an increased risk for these adverse pregnancy outcomes. Due to the limited number of exposed pregnancies and multiple confounding factors (such as underlying maternal conditions, other maternal medications, and gestational timing of exposure), these published case reports and studies do not reliably estimate the frequency, presence or absence of adverse outcomes.

Animal Data

When rats received Epogen at doses greater than or equal to 100 Units/kg/day during mating and through early pregnancy (dosing stopped prior to organogenesis), there were slight increases in the incidences of pre- and post-implantation loss, and a decrease in live fetuses in the presence of maternal toxicity (red limbs/pinna, focal splenic capsular toxicity, increased organ weights). This animal dose level of 100 Units/kg/day may approximate the clinical recommended starting dose, depending on the treatment indication. When pregnant rats and rabbits received intravenous doses of up to 500 mg/kg/day of Epogen only during organogenesis (gestational days 7 to 17 in rats and gestational days 6 to 18 in rabbits), no teratogenic effects were observed in the offspring. The offspring (F1 generation) of the treated rats were observed postnatally; rats from the F1 generation reached maturity and were mated; no Epogen-related effects were apparent for their offspring (F2 generation fetuses).

When pregnant rats received Epogen at doses of 500 Units/kg/day late in pregnancy (after the period of organogenesis from day 17 of gestation through day 21 of lactation), pups exhibited decreased number of caudal vertebrae, decreased body weight gain, and delayed appearance of abdominal hair, eyelid opening, and ossification in the presence of maternal toxicity (red limbs/pinna, increased organ weights). This animal dose level of 500 U/kg/day is approximately five times the clinical recommended starting dose depending on the patient’s treatment indication.

8.2 Lactation

Risk Summary

Epogen from multiple-dose vials contains benzyl alcohol and is contraindicated in lactating women [see Contraindications (4), Warnings and Precautions (5.9)]. Advise a lactating woman not to breastfeed for at least 2 weeks after the last dose. The preservative benzyl alcohol has been associated with serious adverse reactions and death when administered intravenously to neonates and infants [see Use in Specific Populations (8.4)]. There is a potential for similar risks to infants exposed to benzyl alcohol through human milk.

Do not mix Epogen with bacteriostatic saline containing benzyl alcohol, if administering Epogen to a lactating woman [see Dosage and Administration (2.1)].

There is no information regarding the presence of Epogen in human milk, the effects on the breastfed infant, or the effects on milk production. However, endogenous erythropoietin is present in human milk. Because many drugs are present in human milk, caution should be exercised when Epogen from single-dose vials is administered to a lactating woman.

8.4 Pediatric Use

The multiple-dose vials are formulated with benzyl alcohol and are contraindicated for use in neonates and infants [see Contraindications (4), Warnings and Precautions (5.9)]. When therapy with Epogen is needed in neonates and infants, use the single-dose vial, which is a benzyl alcohol-free formulation. Do not mix the single-dose vials with bacteriostatic saline when administering Epogen to neonates or infants because it contains benzyl alcohol [see Dosage and Administration (2.6)].

Serious adverse reactions including fatal reactions and the “gasping syndrome” occurred in premature neonates and infants in the neonatal intensive care unit who received drugs containing benzyl alcohol as a preservative. In these cases, benzyl alcohol dosages of 99 to 234 mg/kg/day produced high levels of benzyl alcohol and its metabolites in the blood and urine (blood levels of benzyl alcohol were 0.61 to 1.378 mmol/L). Additional adverse reactions included gradual neurological deterioration, seizures, intracranial hemorrhage, hematologic abnormalities, skin breakdown, hepatic and renal failure, hypotension, bradycardia, and cardiovascular collapse. Preterm, low birth weight infants may be more likely to develop these reactions because they may be less able to metabolize benzyl alcohol. The minimum amount of benzyl alcohol at which serious adverse reactions may occur is not known [see Warnings and Precautions (5.9)].

Pediatric Patients with CKD

Epogen is indicated in pediatric patients, ages 1 month to 16 years of age, for the treatment of anemia associated with CKD requiring dialysis. Safety and effectiveness in pediatric patients less than 1 month old have not been established [see Clinical Studies (14.1)].

Use of Epogen in pediatric patients with CKD not requiring dialysis is supported by efficacy in pediatric patients requiring dialysis. The mechanism of action of Epogen is the same for these two populations. Published literature also has reported the use of Epogen in pediatric patients with CKD not requiring dialysis. Dose-dependent increases in hemoglobin and hematocrit were observed with reductions in transfusion requirements.

The safety data from the pediatric studies and postmarketing reports are similar to those obtained from the studies of Epogen in adult patients with CKD [see Warnings and Precautions (5) and Adverse Reactions (6.1)]. Postmarketing reports do not indicate a difference in safety profiles in pediatric patients with CKD requiring dialysis and not requiring dialysis.

Pediatric Patients with Cancer on Chemotherapy

Epogen is indicated in patients 5 to 18 years old for the treatment of anemia due to concomitant myelosuppressive chemotherapy. Safety and effectiveness in pediatric patients less than 5 years of age have not been established [see Clinical Studies (14.3)]. The safety data from these studies are similar to those obtained from the studies of Epogen in adult patients with cancer [see Warnings and Precautions (5.1, 5.2) and Adverse Reactions (6.1)].

Pediatric Patients with HIV Infection Receiving Zidovudine

Published literature has reported the use of Epogen in 20 zidovudine-treated, anemic, pediatric patients with HIV infection, ages 8 months to 17 years, treated with 50 to 400 Units/kg subcutaneously or intravenously 2 to 3 times per week. Increases in hemoglobin levels and in reticulocyte counts and decreases in or elimination of RBC transfusions were observed.

Pharmacokinetics in Neonates

Limited pharmacokinetic data from a study of 7 preterm, very low birth weight neonates and 10 healthy adults given intravenous erythropoietin suggested that distribution volume was approximately 1.5 to 2 times higher in the preterm neonates than in the healthy adults, and clearance was approximately 3 times higher in the preterm neonates than in the healthy adults.

8.5 Geriatric Use

Of the 4553 patients who received Epogen in the 6 studies for treatment of anemia due to CKD not receiving dialysis, 2726 (60%) were age 65 years and over, while 1418 (31%) were 75 years and over. Of the 757 patients who received Epogen in the 3 studies of CKD patients on dialysis, 361 (47%) were age 65 years and over, while 100 (13%) were 75 years and over. No differences in safety or effectiveness were observed between geriatric and younger patients. Dose selection and adjustment for an elderly patient should be individualized to achieve and maintain the target hemoglobin [see Dosage and Administration (2)].

Among 778 patients enrolled in the 3 clinical studies of Epogen for the treatment of anemia due to concomitant chemotherapy, 419 received Epogen and 359 received placebo. Of the 419 who received Epogen, 247 (59%) were age 65 years and over, while 78 (19%) were 75 years and over. No overall differences in safety or effectiveness were observed between geriatric and younger patients. The dose requirements for Epogen in geriatric and younger patients within the 3 studies were similar.

Among 1731 patients enrolled in the 6 clinical studies of Epogen for reduction of allogeneic RBC transfusions in patients undergoing elective surgery, 1085 received Epogen and 646 received placebo or standard of care treatment. Of the 1085 patients who received Epogen, 582 (54%) were age 65 years and over, while 245 (23%) were 75 years and over. No overall differences in safety or effectiveness were observed between geriatric and younger patients. The dose requirements for Epogen in geriatric and younger patients within the 4 studies using the 3 times weekly schedule and 2 studies using the weekly schedule were similar.

Insufficient numbers of patients age 65 years or older were enrolled in clinical studies of Epogen for the treatment of patients treated with zidovudine for HIV infection to determine whether they respond differently from younger patients.

9 DRUG ABUSE AND DEPENDENCE

9.1 Controlled Substance

Epogen contains epoetin alfa, which is not a controlled substance.

9.2 Abuse

Abuse is the intentional, non-therapeutic use of a drug, even once, for its desirable psychological or physiological effects. Abuse of Epogen may be seen in athletes for the effects on erythropoiesis. Abuse of drugs that increase erythropoiesis, such as Epogen, by healthy persons may lead to life-threatening cardiovascular complications (e.g., stroke, myocardial infarction, or thromboembolism) [see Warnings and Precautions (5.1)].

In animal studies, epoetin alfa did not distribute to the CNS nor produce behavioral effects that are consistent with CNS activity.

10 OVERDOSAGE

Epogen overdosage can cause hemoglobin levels above the desired level, which should be managed with discontinuation or reduction of Epogen dosage and/or with phlebotomy, as clinically indicated [see Clinical Pharmacology (12.2)]. Cases of severe hypertension have been observed following overdose with ESAs [see Warnings and Precautions (5.3)].

11 DESCRIPTION

Epoetin alfa is a 165-amino acid erythropoiesis-stimulating glycoprotein manufactured by recombinant DNA technology. It has a molecular weight of approximately 30,400 daltons and is produced by mammalian cells into which the human erythropoietin gene has been introduced. The product contains the identical amino acid sequence of isolated natural erythropoietin.

Epogen (epoetin alfa) injection for intravenous or subcutaneous administration is formulated as a sterile, clear, colorless liquid in vials in multiple formulations. Single-dose vials, formulated with an isotonic sodium chloride/sodium citrate-buffered solution, are supplied in multiple strengths. Each single-dose 1 mL vial contains 2,000, 3,000, 4,000, or 10,000 Units of epoetin alfa, Albumin (Human) (2.5 mg), citric acid (0.06 mg), sodium chloride (5.9 mg), and sodium citrate (5.8 mg) in Water for Injection, USP (pH 6.9 ± 0.3). Multiple-dose, 2 mL vials contain 10,000 Units epoetin alfa, albumin (human) (2.5 mg), benzyl alcohol (1%), sodium chloride (8.2 mg), citric acid (0.11 mg), and sodium citrate (1.3 mg) per 1 mL Water for Injection, USP (pH 6.1 ± 0.3). Multiple-dose 1 mL vials contain 20,000 Units epoetin alfa, albumin (human) (2.5 mg), benzyl alcohol (1%), sodium chloride (8.2 mg), citric acid (0.11 mg), and sodium citrate (1.3 mg), per 1 mL in Water for Injection, USP (pH 6.1 ± 0.3).

12 CLINICAL PHARMACOLOGY

12.1 Mechanism of Action

Epogen stimulates erythropoiesis by the same mechanism as endogenous erythropoietin.

12.2 Pharmacodynamics

Epogen increases the reticulocyte count within 10 days of initiation, followed by increases in the RBC count, hemoglobin, and hematocrit, usually within 2 to 6 weeks. The rate of hemoglobin increase varies among patients and is dependent upon the dose of Epogen administered. For correction of anemia in hemodialysis patients, a greater biologic response is not observed at doses exceeding 300 Units/kg 3 times weekly.

12.3 Pharmacokinetics

In adult and pediatric patients with CKD, the elimination half-life (t1/2) of plasma erythropoietin after intravenous administration of Epogen ranged from 4 to 13 hours. After subcutaneous administration, Cmax was achieved within 5 to 24 hours. The t1/2 in adult patients with serum creatinine greater than 3 mg/dL was similar between those not on dialysis and those maintained on dialysis. The pharmacokinetic data indicate no apparent difference in Epogen t1/2 among adult patients above or below 65 years of age.

A pharmacokinetic study comparing 150 Units/kg subcutaneous 3 times weekly to 40,000 Units subcutaneous weekly dosing regimen was conducted for 4 weeks in healthy subjects (n = 12) and for 6 weeks in anemic cancer patients (n = 32) receiving cyclic chemotherapy. There was no accumulation of serum erythropoietin after the 2 dosing regimens during the study period. The 40,000 Units weekly regimen had a higher Cmax (3- to 7-fold), longer Tmax (2- to 3-fold), higher AUC0-168 h (2- to 3-fold) of erythropoietin and lower clearance (CL) (50%) than the 150 Units/kg 3 times weekly regimen. In anemic cancer patients, the average t1/2 was similar (40 hours with range of 16 to 67 hours) after both dosing regimens. After the 150 Units/kg 3 times weekly dosing, the values of Tmax and CL were similar (13.3 ± 12.4 vs. 14.2 ± 6.7 hours, and 20.2 ± 15.9 vs. 23.6 ± 9.5 mL/hr/kg) between week 1 when patients were receiving chemotherapy (n = 14) and week 3 when patients were not receiving chemotherapy (n = 4). Differences were observed after the 40,000 Units weekly dosing with longer Tmax (38 ± 18 hours) and lower CL (9.2 ± 4.7 mL/hr/kg) during week 1 when patients were receiving chemotherapy (n = 18) compared with those (22 ± 4.5 hours, 13.9 ± 7.6 mL/hr/kg, respectively) during week 3 when patients were not receiving chemotherapy (n = 7).

The pharmacokinetic profile of Epogen in pediatric patients appeared similar to that of adults.

The pharmacokinetics of Epogen has not been studied in patients with HIV infection.

13 NONCLINICAL TOXICOLOGY

13.1 Carcinogenesis, Mutagenesis, Impairment of Fertility

The carcinogenic potential of Epogen has not been evaluated.

Epogen was not mutagenic or clastogenic under the conditions tested: Epogen was negative in the in vitro bacterial reverse mutation assay (Ames test), in the in vitro mammalian cell gene mutation assay (the hypoxanthine-guanine phosphoribosyl transferase [HGPRT] locus), in an in vitro chromosomal aberration assay in mammalian cells, and in the in vivo mouse micronucleus assay.

When administered intravenously to male and female rats prior to and during mating, and to females through the beginning of implantation (up to gestational day 7; dosing stopped prior to the beginning of organogenesis), doses of 100 and 500 Units/kg/day of Epogen caused slight increases in pre-implantation loss, post-implantation loss and decreases in the incidence of live fetuses. It is not clear whether these effects reflect a drug effect on the uterine environment or on the conceptus. This animal dose level of 100 Units/kg/day approximates the clinical recommended starting dose, depending on the patient’s treatment indication, but may be lower than the clinical dose in patients whose doses have been adjusted.

14 CLINICAL STUDIES

14.1 Patients with Chronic Kidney Disease

Adult Patients on Dialysis

Patients with chronic kidney disease on dialysis: ESA effects on rates of transfusion

In clinical studies of patients with CKD on dialysis, Epogen increased hemoglobin levels and decreased the need for RBC transfusion. Overall, more than 95% of patients were RBC transfusion-independent after receiving Epogen for 3 months. In clinical studies at starting doses of 50 to 150 Units/kg 3 times weekly, adult patients responded with an average rate of hemoglobin rise as presented in Table 8.

Table 8. Average Rate of Hemoglobin Rise in 2 Weeks
Starting Dose (3 Times Weekly Intravenously) | Hemoglobin Increase in 2 Weeks
50 Units/kg | 0.5 g/dL
100 Units/kg | 0.8 g/dL
150 Units/kg | 1.2 g/dL

The safety and efficacy of Epogen were evaluated in 13 clinical studies involving intravenous administration to a total of 1010 patients on dialysis with anemia. Overall, more than 90% of the patients treated with Epogen experienced improvement in hemoglobin concentrations. In the 3 largest of these clinical studies, the median maintenance dose necessary to maintain the hemoglobin between 10 to 12 g/dL was approximately 75 Units/kg 3 times weekly. More than 95% of patients were able to avoid RBC transfusions. In the largest U.S. multicenter study, approximately 65% of the patients received doses of 100 Units/kg 3 times weekly or less to maintain their hemoglobin at approximately 11.7 g/dL. Almost 10% of patients received a dose of 25 Units/kg or less, and approximately 10% received a dose of more than 200 Units/kg 3 times weekly to maintain their hemoglobin at this level.

In the Normal Hematocrit Study, the yearly transfusion rate was 51.5% in the lower hemoglobin group (10 g/dL) and 32.4% in the higher hemoglobin group (14 g/dL).

Other ESA trials

In a 26-week, double-blind, placebo-controlled study, 118 patients on dialysis with an average hemoglobin of approximately 7 g/dL were randomized to either Epogen or placebo. By the end of the study, average hemoglobin increased to approximately 11 g/dL in the Epogen-treated patients and remained unchanged in patients receiving placebo. Epogen-treated patients experienced improvements in exercise tolerance and patient-reported physical functioning at month 2 that were maintained throughout the study.

A multicenter, unit-dose study was also conducted in 119 patients receiving peritoneal dialysis who self-administered Epogen subcutaneously. Patients responded to Epogen administered subcutaneously in a manner similar to patients receiving intravenous administration.

Pediatric Patients with CKD on Dialysis

The safety and efficacy of Epogen were studied in a placebo-controlled, randomized study of 113 pediatric patients with anemia (hemoglobin ≤ 9 g/dL) undergoing peritoneal dialysis or hemodialysis. The initial dose of Epogen was 50 Units/kg intravenously or subcutaneously 3 times weekly. The dose of study drug was titrated to achieve either a hemoglobin of 10 to 12 g/dL or an absolute increase in hemoglobin of 2 g/dL over baseline.

At the end of the initial 12 weeks, a statistically significant rise in mean hemoglobin (3.1 g/dL vs. 0.3 g/dL) was observed only in the Epogen arm. The proportion of pediatric patients achieving a hemoglobin of 10 g/dL, or an increase in hemoglobin of 2 g/dL over baseline, at any time during the first 12 weeks was higher in the Epogen arm (96% vs. 58%). Within 12 weeks of initiating Epogen therapy, 92.3% of the pediatric patients were RBC transfusion independent as compared to 65.4% who received placebo. Among patients who received 36 weeks of Epogen, hemodialysis patients received a higher median maintenance dose [167 Units/kg/week (n = 28) vs. 76 Units/kg/week (n = 36)] and took longer to achieve a hemoglobin of 10 to 12 g/dL (median time to response 69 days vs. 32 days) than patients undergoing peritoneal dialysis.

Adult Patients with CKD Not Requiring Dialysis

Four clinical studies were conducted in patients with CKD not on dialysis involving 181 patients treated with Epogen. These patients responded to Epogen therapy in a manner similar to that observed in patients on dialysis. Patients with CKD not on dialysis demonstrated a dose-dependent and sustained increase in hemoglobin when Epogen was administered by either an intravenous or subcutaneous route, with similar rates of rise of hemoglobin when Epogen was administered by either route.

Patients with chronic kidney disease not on dialysis: ESA effects on rates of transfusion

In TREAT, a randomized, double-blind trial of 4038 patients with CKD and type 2 diabetes not on dialysis, a post-hoc analysis showed that the proportion of patients receiving RBC transfusions was lower in patients administered an ESA to target a hemoglobin of 13 g/dL compared to the control arm in which an ESA was administered intermittently if hemoglobin concentration decreased to less than 9 g/dL (15% vs. 25%, respectively). In CHOIR, a randomized open-label study of 1432 patients with CKD not on dialysis, use of epoetin alfa to target a higher (13.5 g/dL) versus lower (11.3 g/dL) hemoglobin goal did not reduce the use of RBC transfusions. In each trial, no benefits occurred for the cardiovascular or end-stage renal disease outcomes. In each trial, the potential benefit of ESA therapy was offset by worse cardiovascular safety outcomes resulting in an unfavorable benefit-risk profile [see Warnings and Precautions (5.1)].

ESA Effects on Rates of Death and Other Serious Cardiac Adverse Reactions

Three randomized outcome trials (Normal Hematocrit Study [NHS], Correction of Anemia with Epoetin Alfa in Chronic Kidney Disease [CHOIR], and Trial of Darbepoetin Alfa in Type 2 Diabetes and CKD [TREAT]) have been conducted in patients with CKD using Epogen/PROCRIT/Aranesp to target higher vs. lower hemoglobin levels. Though these trials were designed to establish a cardiovascular or renal benefit of targeting higher hemoglobin levels, in all 3 studies, patients randomized to the higher hemoglobin target experienced worse cardiovascular outcomes and showed no reduction in progression to ESRD. In each trial, the potential benefit of ESA therapy was offset by worse cardiovascular safety outcomes resulting in an unfavorable benefit-risk profile [see Warnings and Precautions (5.1)].

14.2 Zidovudine-treated Patients with HIV Infection

The safety and efficacy of Epogen were evaluated in 4 placebo-controlled studies enrolling 297 anemic patients (hemoglobin < 10 g/dL) with HIV infection receiving concomitant therapy with zidovudine. In the subgroup of patients (89/125 Epogen and 88/130 placebo) with pre-study endogenous serum erythropoietin levels ≤ 500 mUnits/mL, Epogen reduced the mean cumulative number of units of blood transfused per patient by approximately 40% as compared to the placebo group. Among those patients who required RBC transfusions at baseline, 43% of patients treated with Epogen versus 18% of placebo-treated patients were RBC transfusion-independent during the second and third months of therapy. Epogen therapy also resulted in significant increases in hemoglobin in comparison to placebo. When examining the results according to the weekly dose of zidovudine received during month 3 of therapy, there was a statistically significant reduction (p < 0.003) in RBC transfusion requirements in patients treated with Epogen (n = 51) compared to placebo-treated patients (n = 54) whose mean weekly zidovudine dose was ≤ 4200 mg/week.

Approximately 17% of the patients with endogenous serum erythropoietin levels ≤ 500 mUnits/mL receiving Epogen in doses from 100 to 200 Units/kg 3 times weekly achieved a hemoglobin of 12.7 g/dL without administration of RBC transfusions or significant reduction in zidovudine dose. In the subgroup of patients whose pre-study endogenous serum erythropoietin levels were > 500 mUnits/mL, Epogen therapy did not reduce RBC transfusion requirements or increase hemoglobin compared to the corresponding responses in placebo-treated patients.

14.3 Patients with Cancer on Chemotherapy

The safety and effectiveness of Epogen was assessed in two multicenter, randomized (1:1), placebo-controlled, double-blind studies (Study C1 and Study C2) and a pooled analysis of six additional randomized (1:1), multicenter, placebo-controlled, double-blind studies. All studies were conducted in patients with anemia due to concomitantly administered cancer chemotherapy. Study C1 enrolled 344 adult patients, Study C2 enrolled 222 pediatric patients, and the pooled analysis contained 131 patients randomized to epoetin alfa or placebo. In Studies C1 and C2, efficacy was demonstrated by a reduction in the proportion of patients who received an RBC transfusion, from week 5 through end of the study, with the last-known RBC transfusion status carried forward for patients who discontinued treatment. In the pooled analysis, efficacy was demonstrated by a reduction in the proportion of patients who received an RBC transfusion from week 5 through end of the study in the subset of patients who were remaining on therapy for 6 or more weeks.

Study C1

Study C1 was conducted in patients with anemia (hemoglobin < 11.5 g/dL for males; < 10.5 g/dL for females) with non-myeloid malignancies receiving myelosuppressive chemotherapy. Randomization was stratified by type of malignancy (lung vs. breast vs. other), concurrent radiation therapy planned (yes or no), and baseline hemoglobin (< 9 g/dL vs. ≥ 9 g/dL); patients were randomized to epoetin alfa 40,000 Units (n = 174) or placebo (n = 170) as a weekly subcutaneous injection commencing on the first day of the chemotherapy cycle.

Ninety-one percent of patients were white, 44% were male, and the median age of patients was 66 years (range: 20 to 88 years). The proportion of patients withdrawn from the study prior to week 5 was less than 10% for placebo-treated or epoetin-treated patients. Per protocol, the last available hemoglobin values from patients who dropped out were included in the efficacy analyses. Efficacy results are shown in Table 9.

Table 9. Study C1: Proportion of Patients Transfused
 | Week 5 Through Week 16 or End of Study [Last-known RBC transfusion status carried forward for patients who discontinued treatment.]
Chemotherapy Regimen | Epogen (n = 174) | Placebo (n = 170)
All Regimens | 14% (25/174) [Two-sided p < 0.001, logistic regression analysis adjusting for accrual rate and stratification variables.] | 28% (48/170)
Regimens without cisplatin | 14% (21/148) | 26% (35/137)
Regimens containing cisplatin | 15% (4/26) | 39% (13/33)

Study C2

Study C2 was conducted in 222 patients with anemia, ages 5 to 18, receiving chemotherapy for the treatment of various childhood malignancies. Randomization was stratified by cancer type (solid tumors, Hodgkin’s disease, acute lymphocytic leukemia, vs. non-Hodgkin’s lymphoma); patients were randomized to receive epoetin alfa at 600 Units/kg maximum 40,000 Units (n = 111) or placebo (n = 111) as a weekly intravenous injection.

Sixty-nine percent of patients were white, 55% were male, and the median age of patients was 12 years (range: 5 to 18 years). Two (2%) of placebo-treated patients and 3 (3%) of epoetin alfa-treated patients dropped out of the study prior to week 5. There were fewer RBC transfusions from week 5 through the end-of-study in epoetin alfa-treated patients [51% (57/111)] compared to placebo-treated patients [69% (77/111)]. There was no evidence of an improvement in health-related quality of life, including no evidence of an effect on fatigue, energy, or strength in patients receiving Epogen as compared to those receiving placebo.

Pooled Analysis (Three Times Per Week Dosing)

The results of 6 studies of similar design and that randomized 131 patients to epoetin alfa or placebo were pooled to assess the safety and effectiveness of epoetin alfa. Patients were randomized to receive epoetin alfa at 150 Units/kg (n = 63) or placebo (n = 68), subcutaneously three times per week for 12 weeks in each study. Across all studies, 72 patients were treated with concomitant non cisplatin-containing chemotherapy regimens and 59 patients were treated with concomitant cisplatin-containing chemotherapy regimens. Twelve patients (19%) in the epoetin alfa arm and 10 patients (15%) in the placebo-arm dropped out prior to week 6 and are excluded from efficacy analyses.

Table 10. Proportion of Patients Transfused in the Pooled Analysis for Three Times Per Week Dosing
 | Week 5 Through Week 12 or End of Study [Limited to patients remaining on study beyond week 6 and includes only RBC transfusions during weeks 5-12.]
Chemotherapy Regimen | Epogen | Placebo
All Regimens | 22% (11/51) [Two-sided p < 0.05, unadjusted.] | 43% (25/58)
Regimens without cisplatin | 21% (6/29) | 33% (11/33)
Regimens containing cisplatin | 23% (5/22) | 56% (14/25)

14.4 Surgery Patients

The safety and efficacy of Epogen were evaluated in a placebo-controlled, double-blind study (S1) enrolling 316 patients scheduled for major, elective orthopedic hip or knee surgery who were expected to require ≥ 2 units of blood and who were not able or willing to participate in an autologous blood donation program. Patients were stratified into 1 of 3 groups based on their pretreatment hemoglobin [≤ 10 g/dL (n = 2), > 10 to ≤ 13 g/dL (n = 96), and > 13 to ≤ 15 g/dL (n = 218)] and then randomly assigned to receive 300 Units/kg Epogen, 100 Units/kg Epogen, or placebo by subcutaneous injection for 10 days before surgery, on the day of surgery, and for 4 days after surgery. All patients received oral iron and a low-dose, postoperative warfarin regimen.

Treatment with Epogen 300 Units/kg significantly (p = 0.024) reduced the risk of allogeneic RBC transfusion in patients with a pretreatment hemoglobin of > 10 to ≤ 13 g/dL; 5/31 (16%) of patients treated with Epogen 300 Units/kg, 6/26 (23%) of patients treated with Epogen 100 Units/kg, and 13/29 (45%) of placebo-treated patients were transfused. There was no significant difference in the number of patients transfused between Epogen (9% 300 Units/kg, 6% 100 Units/kg) and placebo (13%) in the > 13 to ≤ 15 g/dL hemoglobin stratum. There were too few patients in the ≤ 10 g/dL group to determine if Epogen is useful in this hemoglobin strata. In the > 10 to ≤ 13 g/dL pretreatment stratum, the mean number of units transfused per Epogen-treated patient (0.45 units blood for 300 Units/kg, 0.42 units blood for 100 Units/kg) was less than the mean transfused per placebo-treated patient (1.14 units) (overall p = 0.028). In addition, mean hemoglobin, hematocrit, and reticulocyte counts increased significantly during the presurgery period in patients treated with Epogen.

Epogen was also evaluated in an open-label, parallel-group study (S2) enrolling 145 patients with a pretreatment hemoglobin level of ≥ 10 to ≤ 13 g/dL who were scheduled for major orthopedic hip or knee surgery and who were not participating in an autologous program. Patients were randomly assigned to receive 1 of 2 subcutaneous dosing regimens of Epogen (600 Units/kg once weekly for 3 weeks prior to surgery and on the day of surgery, or 300 Units/kg once daily for 10 days prior to surgery, on the day of surgery, and for 4 days after surgery). All patients received oral iron and appropriate pharmacologic anticoagulation therapy.

From pretreatment to presurgery, the mean increase in hemoglobin in the 600 Units/kg weekly group (1.44 g/dL) was greater than that observed in the 300 Units/kg daily group. The mean increase in absolute reticulocyte count was smaller in the weekly group (0.11 × 10^6/mm^3) compared to the daily group (0.17 × 10^6/mm^3). Mean hemoglobin levels were similar for the 2 treatment groups throughout the postsurgical period.

The erythropoietic response observed in both treatment groups resulted in similar RBC transfusion rates [11/69 (16%) in the 600 Units/kg weekly group and 14/71 (20%) in the 300 Units/kg daily group]. The mean number of units transfused per patient was approximately 0.3 units in both treatment groups.

16 HOW SUPPLIED/STORAGE AND HANDLING

Epogen (epoetin alfa) injection is a sterile, clear, and colorless solution available as:

Preservative-free, single-dose vials (in citrate-buffered formulation): 2,000 Units/mL (NDC 55513-126-10, NDC 55513-126-20), 3,000 Units/mL (NDC 55513-267-10, NDC 55513-267-20), 4,000 Units/mL (NDC 55513-148-10, NDC 55513-148-20), or 10,000 Units/mL (NDC 55513-144-10, NDC 55513-144-20) supplied in dispensing packs containing ten 1 mL single-dose vials.

Preserved, multiple-dose vial: 20,000 Units/2 mL (10,000 Units/mL) (NDC 55513-283-10, NDC 55513-283-20) supplied in dispensing packs containing ten 2 mL multiple-dose vials.

Preserved, multiple-dose vial: 20,000 Units/mL (NDC 55513-478-10, NDC 55513-478-20) supplied in dispensing packs containing ten 1 mL multiple-dose vials.

Store at 36°F to 46°F (2°C to 8°C). Do not freeze.

Do not shake. Do not use Epogen that has been shaken or frozen.

Store Epogen vials in the original carton until use to protect from light.

17 PATIENT COUNSELING INFORMATION

Advise the patient to read the FDA-approved patient labeling (Medication Guide and Instructions for Use).

Inform patients:

- Of the increased risks of mortality, serious cardiovascular reactions, thromboembolic reactions, stroke, and tumor progression [see Warnings and Precautions (5.1, 5.2)].
- To undergo regular blood pressure monitoring, adhere to prescribed anti-hypertensive regimen and follow recommended dietary restrictions.
- To contact their healthcare provider for new-onset neurologic symptoms or change in seizure frequency.
- Of the need to have regular laboratory tests for hemoglobin.
- Risks are associated with benzyl alcohol in neonates, infants, pregnant women, and lactating women [see Use in Specific Populations (8.1, 8.2, 8.4)].

Instruct patients who self-administer Epogen of the:

- Importance of following the Instructions for Use.
- Dangers of reusing needles, syringes, or unused portions of single-dose vials.
- Proper disposal of used syringes, needles, and unused vials, and of the full container.

EPOGEN® (epoetin alfa)

Manufactured by:
Amgen Inc.
One Amgen Center Drive
Thousand Oaks, CA 91320-1799 U.S.A.
U.S. License Number 1080

©1989-2018, 2024 Amgen Inc. All rights reserved.

1xxxxxx- v35

MEDICATION GUIDE
EPOGEN® (Ee-po-jen)
(epoetin alfa)

Read this Medication Guide:

- before you start Epogen.
- if you are told by your healthcare provider that there is new information about Epogen.
- if you are told by your healthcare provider that you may inject Epogen at home, read this Medication Guide each time you receive a new supply of medicine.

This Medication Guide does not take the place of talking to your healthcare provider about your medical condition or your treatment. Talk with your healthcare provider regularly about the use of Epogen and ask if there is new information about Epogen.

What is the most important information I should know about Epogen?
Epogen may cause serious side effects that can lead to death, including:
For people with cancer:

- Your tumor may grow faster and you may die sooner if you choose to take Epogen. Your healthcare provider will talk with you about these risks.

For all people who take Epogen, including people with cancer or chronic kidney disease:

- Serious heart problems, such as heart attack or heart failure, and stroke. You may die sooner if you are treated with Epogen to increase red blood cells (RBCs) to near the same level found in healthy people.
- Blood clots. Blood clots may happen at any time while taking Epogen. If you are receiving Epogen for any reason and you are going to have surgery, talk to your healthcare provider about whether or not you need to take a blood thinner to lessen the chance of blood clots during or following surgery. Blood clots can form in blood vessels (veins), especially in your leg (deep venous thrombosis or DVT). Pieces of a blood clot may travel to the lungs and block the blood circulation in the lungs (pulmonary embolus).
- Call your healthcare provider or get medical help right away if you have any of these symptoms:
  • Chest pain
  • Trouble breathing or shortness of breath
  • Pain in your legs, with or without swelling
  • A cool or pale arm or leg
  • Sudden confusion, trouble speaking, or trouble understanding others’ speech
  • Sudden numbness or weakness in your face, arm, or leg, especially on one side of your body
  • Sudden trouble seeing
  • Sudden trouble walking, dizziness, loss of balance or coordination
  • Loss of consciousness (fainting)
  • Hemodialysis vascular access stops working

See “What are the possible side effects of Epogen?” below for more information.
If you decide to take Epogen, your healthcare provider should prescribe the smallest dose of Epogen that is necessary to reduce your chance of needing RBC transfusions.

What is Epogen?
Epogen is a prescription medicine used to treat anemia. People with anemia have a lower-than-normal number of RBCs. Epogen works like the human protein called erythropoietin to help your body make more RBCs. Epogen is used to reduce or avoid the need for RBC transfusions.
Epogen may be used to treat anemia if it is caused by:

- Chronic kidney disease (you may or may not be on dialysis).
- Chemotherapy that will be used for at least two months after starting Epogen.
- A medicine called zidovudine (AZT) used to treat HIV infection.

Epogen may also be used to reduce the chance you will need RBC transfusions if you are scheduled for certain surgeries where a lot of blood loss is expected.
If your hemoglobin level stays too high or if your hemoglobin goes up too quickly, this may lead to serious health problems which may result in death. These serious health problems may happen if you take Epogen, even if you do not have an increase in your hemoglobin level.
Epogen has not been proven to improve quality of life, fatigue, or well-being.
Epogen should not be used for treatment of anemia:

- If you have cancer and you will not be receiving chemotherapy that may cause anemia.
- If you have a cancer that has a high chance of being cured. Talk with your healthcare provider about the kind of cancer you have.
- If your anemia caused by chemotherapy treatment can be managed by RBC transfusion.
- In place of emergency treatment for anemia (RBC transfusions).

Epogen should not be used to reduce the chance you will need RBC transfusions if:

- You are scheduled for surgery on your heart or blood vessels.
- You are able and willing to donate blood prior to surgery.

It is not known if Epogen is safe and effective in treating anemia in children less than 1 month old who have chronic kidney disease and in children less than 5 years old who have anemia caused by chemotherapy.

Who should not take Epogen?
Do not take Epogen if you:

- Have cancer and have not been counseled by your healthcare provider about treatment with Epogen.
- Have high blood pressure that is not controlled (uncontrolled hypertension).
- Have been told by your healthcare provider that you have or have ever had a type of anemia called Pure Red Cell Aplasia (PRCA) that starts after treatment with Epogen or other erythropoietin protein medicines.
- Have had a serious allergic reaction to Epogen.

Do not give Epogen from multiple-dose vials to:

- Pregnant or breastfeeding women
- Babies

Before taking Epogen, tell your healthcare provider about all of your medical conditions, including if you:

- Have heart disease.
- Have high blood pressure.
- Have had a seizure (convulsion) or stroke.
- Receive dialysis treatment.
- Are pregnant or plan to become pregnant. It is not known if Epogen may harm your unborn baby. Talk to your healthcare provider about possible pregnancy and birth control choices that are right for you.
- Are breastfeeding or plan to breastfeed. It is not known if Epogen passes into breast milk.

Tell your healthcare provider about all the medicines you take, including prescription and over-the-counter medicines, vitamins, and herbal supplements.

How should I take Epogen?

- If you or your caregiver has been trained to give Epogen shots (injections) at home:
  • Be sure that you read, understand, and follow the “Instructions for Use” that come with Epogen.
  • Take Epogen exactly as your healthcare provider tells you to. Do not change the dose of Epogen unless told to do so by your healthcare provider.
  • Your healthcare provider will show you how much Epogen to use, how to inject it, how often it should be injected, and how to safely throw away the used vials, syringes, and needles.
  • If you miss a dose of Epogen, call your healthcare provider right away and ask what to do.
  • If you take more than the prescribed dose of Epogen, call your healthcare provider right away.
- During treatment with Epogen, continue to follow your healthcare provider’s instructions for diet and medicines.
- Have your blood pressure checked as instructed by your healthcare provider.

What are the possible side effects of Epogen?
Epogen may cause serious side effects, including:

- See “What is the most important information I should know about Epogen?”
- High blood pressure. High blood pressure is a common side effect of Epogen in people with chronic kidney disease. Your blood pressure may go up or be difficult to control with blood pressure medicine while taking Epogen. This can happen even if you have never had high blood pressure before. Your healthcare provider should check your blood pressure often. If your blood pressure does go up, your healthcare provider may prescribe new or more blood pressure medicine.
- Seizures. If you have any seizures while taking Epogen, get medical help right away and tell your healthcare provider.
- Antibodies to Epogen. Your body may make antibodies to Epogen. These antibodies can block or lessen your body’s ability to make RBCs and cause you to have severe anemia. Call your healthcare provider if you have unusual tiredness, lack of energy, dizziness, or fainting. You may need to stop taking Epogen.
- Serious allergic reactions. Serious allergic reactions can cause a skin rash, itching, shortness of breath, wheezing, dizziness and fainting because of a drop in blood pressure, swelling around your mouth or eyes, fast pulse, or sweating. If you have a serious allergic reaction, stop using Epogen and call your healthcare provider or get medical help right away.
- Severe skin reactions. Signs and symptoms of severe skin reactions with Epogen may include: skin rash with itching, blisters, skin sores, peeling, or areas of skin coming off. If you have any signs or symptoms of a severe skin reaction, stop using Epogen and call your healthcare provider or get medical help right away.
- Dangers of using Epogen from multiple-dose vials in newborns, infants, and pregnant or breastfeeding women. Do not use Epogen from multiple-dose vials in newborns, infants, pregnant or breastfeeding women because the Epogen in these vials contains benzyl alcohol. Benzyl alcohol has been shown to cause brain damage, other serious side effects, and death in newborn and premature babies. If you use Epogen from multiple-dose vials you should not breastfeed for at least 2 weeks after the last dose. Epogen that comes in single-dose vials does not contain benzyl alcohol. See “Who should not take Epogen?”

Common side effects of Epogen include:

• joint, muscle, or bone pain

• rash

• soreness of mouth

• fever

• nausea

• itching

• cough

• vomiting

• headache

• dizziness

• blood vessel blockage

• respiratory infection

• high blood sugar

• low white blood cells

• weight decrease

• low potassium levels in the blood

• trouble sleeping

• depression

• chills

• difficulty swallowing

• muscle spasm

• redness and pain at the Epogen injection site
These are not all of the possible side effects of Epogen. Your healthcare provider can give you a more complete list. Tell your healthcare provider about any side effects that bother you or that do not go away.
Call your doctor for medical advice about side effects. You may report side effects to FDA at 1-800-FDA-1088.

How should I store Epogen?

- Do not shake Epogen.
- Store Epogen vials in the carton it comes in to protect from light.
- Store Epogen in the refrigerator between 36°F to 46°F (2°C to 8°C).
- Do not freeze Epogen. Do not use Epogen that has been frozen.
- Throw away multiple-dose vials of Epogen no later than 21 days from the first day that you put a needle into the vial.
- Single-dose vials of Epogen should be used only one time. Throw the vial away after use even if there is medicine left in the vial.

Keep Epogen and all medicines out of the reach of children.

General information about the safe and effective use of Epogen
Medicines are sometimes prescribed for purposes other than those listed in a Medication Guide. Do not use Epogen for a condition for which it was not prescribed. Do not give Epogen to other people even if they have the same symptoms that you have. It may harm them. You can ask your healthcare provider or pharmacist for information about Epogen that is written for healthcare professionals.

What are the ingredients in Epogen?
Active ingredient: epoetin alfa
Inactive ingredients:

- Multiple-dose vials contain benzyl alcohol.
- All vials contain albumin (human), citric acid, sodium chloride, sodium citrate, and Water for Injection.

Manufactured by: Amgen Inc. One Amgen Center Drive Thousand Oaks, CA 91320-1799 U.S.A.
©1989-2017, 2024 Amgen Inc. All rights reserved. 1xxxxxx- v10
For more information, go to the following website: www.epogen.com or call 1-800-77-AMGEN

This Medication Guide has been approved by the U.S. Food and Drug Administration Revised: 12/2024

PATIENT INFORMATION

Instructions for Use
EPOGEN® (Ee-po-jen)
(epoetin alfa)

Use these Instructions for Use if you or your caregiver has been trained to give Epogen injections at home. Do not give yourself the injection unless you have received training from your healthcare provider. If you are not sure about giving the injection or you have questions, ask your healthcare provider for help.

Before reading these Instructions for Use, read the Medication Guide that comes with Epogen for the most important information you need to know.

When you receive your Epogen vial and syringes make sure that:

- The name Epogen appears on the carton and vial label.
- The expiration date on the vial label has not passed. Do not use a vial of Epogen after the expiration date on the label.
- The dose strength of the Epogen vial (number of Units per mL on the vial label) is the same as your healthcare provider prescribed.
- You understand what the dose strength of Epogen means. Epogen vials come in several dose strengths. For example, the dose strength may be described as 10,000 Units/mL on the vial label. This strength means that 10,000 Units of medicine are contained in each 1 mL (milliliter) of liquid. Your healthcare provider may also refer to a mL as a “cc.” One mL is the same as one “cc.”
- The Epogen liquid in the vial is clear and colorless. Do not use Epogen if the liquid in the vial looks discolored or cloudy, or if the liquid has lumps, flakes, or particles.
- The Epogen vial has a color cap on the top of the vial. Do not use a vial of Epogen if the color cap on the top of the vial has been removed or is missing.
- Use only the type of disposable syringe and needle that your healthcare provider has prescribed.
- Do not shake Epogen. Shaking could cause Epogen not to work. If you shake Epogen, the solution in the vial may look foamy and should not be used.
- Do not freeze Epogen. Do not use a vial of Epogen that has been frozen.
- Store Epogen in the refrigerator between 36°F to 46°F (2°C to 8°C).
- Keep Epogen away from light.
- Single-dose vials of Epogen should be used only one time. Throw the vial away after use even if there is medicine left in the vial.
- After removing a dose from the multidose vial, store the vial in the refrigerator (but not the freezer). Do not store the vial for more than 21 days.
- Throw away the multidose vial as directed by your healthcare provider:
  - if there is not enough medicine left in the multidose vial for another dose, or
  - if it has been more than 21 days since you first put a needle into the multidose vial.

How should I prepare for an injection of Epogen?

- Always keep an extra syringe and needle on hand.
- Follow your healthcare provider’s instructions on how to measure your dose of Epogen. This dose will be measured in Units per mL or cc (1 mL is the same as 1 cc). Use a syringe that is marked in tenths of mL (for example, 0.2 mL or 0.2 cc). Using the wrong syringe can lead to a mistake in your dose and you could inject too much or too little Epogen.

Only use disposable syringes and needles. Use the syringes and needles only one time and then throw them away as instructed by your healthcare provider.

What do I need to know about the different types of Epogen vials?

Epogen comes in two different types of vials.

- Single-dose Vials
- Multidose Vials

The multidose vial of Epogen contains the preservative benzyl alcohol. Benzyl alcohol has been shown to cause brain damage, other serious side effects, and death in newborn and premature babies. Epogen that comes in single-dose vials does not contain benzyl alcohol.

Important: Follow these instructions exactly to help avoid infections.

Preparing the dose:

1. Remove the vial of Epogen from the refrigerator. During this time, protect the solution from light.

2. Do not use a single-dose vial of Epogen more than one time.

3. Do not shake Epogen.

4. Gather the other supplies you will need for your injection (vial, syringe, alcohol wipes, cotton ball, and a puncture-proof container for throwing away the syringe and needle). See Figure 1.

5. Check the date on the Epogen vial to be sure that the drug has not expired.

6. Wash your hands well with soap and water before preparing the medicine. See Figure 2.

7. Flip off the protective color cap on the top of the vial. Do not remove the grey rubber stopper. Wipe the top of the grey rubber stopper with an alcohol wipe. See Figures 3 and 4.

8. Check the package containing the syringe. If the package has been opened or damaged, do not use that syringe. Throw away the syringe in the puncture-proof disposable container. If the syringe package is undamaged, open the package and remove the syringe.

9. Using a syringe and needle that has been recommended by your healthcare provider, carefully remove the needle cover. See Figure 5. Then draw air into the syringe by pulling back on the plunger. The amount of air drawn into the syringe should be equal to the amount (mL or cc) of the Epogen dose prescribed by your healthcare provider. See Figure 6.

10. With the vial on a flat work surface, insert the needle straight down through the grey rubber stopper of the Epogen vial. See Figure 7.

11. Push the plunger of the syringe down to inject the air from the syringe into the vial of Epogen. The air injected into the vial will allow Epogen to be easily withdrawn into the syringe. See Figure 7.

12. Keep the needle inside the vial. Turn the vial and syringe upside down. Be sure the tip of the needle is in the Epogen liquid. Keep the vial upside down. Slowly pull back on the plunger to fill the syringe with Epogen liquid to the number (mL or cc) that matches the dose your healthcare provider prescribed. See Figure 8.

13. Keep the needle in the vial. Check for air bubbles in the syringe. A small amount of air is harmless. Too large an air bubble will give you the wrong Epogen dose. To remove air bubbles, gently tap the syringe with your fingers until the air bubbles rise to the top of the syringe. Slowly push the plunger up to force the air bubbles out of the syringe. Keep the tip of the needle in the Epogen liquid. Pull the plunger back to the number on the syringe that matches your dose. Check again for air bubbles. If there are still air bubbles, repeat the steps above to remove them. See Figures 9 and 10.

14. Double-check that you have the correct dose in the syringe. Lay the vial down on its side with the needle still in it until after you have selected and prepared your site for injection.

Selecting and preparing the injection site:

Epogen can be injected into your body using two different ways (routes) as described below. Follow your healthcare provider’s instructions about how you should inject Epogen. In patients on hemodialysis, the intravenous (IV) route is recommended.

1. Subcutaneous Route:

- Epogen can be injected directly into a layer of fat under your skin. This is called a subcutaneous injection. When giving subcutaneous injections, follow your healthcare provider’s instructions about changing the site for each injection. You may wish to write down the site where you have injected.
- Do not inject Epogen into an area that is tender, red, bruised, hard, or has scars or stretch marks. Recommended sites for injection are shown in Figure 11 below, including:
  - The outer area of the upper arms
  - The abdomen (except for the 2-inch area around the navel)
  - The front of the middle thighs
  - The upper outer area of the buttocks

• Clean the skin with an alcohol wipe where the injection is to be made. Be careful not to touch the skin that has been wiped clean. See Figure 12.

• Double-check that the correct amount of Epogen is in the syringe.

• Remove the prepared syringe and needle from the vial of Epogen and hold it in the hand that you will use to inject the medicine.

• Use the other hand to pinch a fold of skin at the cleaned injection site. Do not touch the cleaned area of skin. See Figure 13.

• Hold the syringe like you would hold a pencil. Use a quick “dart-like” motion to insert the needle either straight up and down (90-degree angle) or at a slight angle (45 degrees) into the skin. Inject the prescribed dose subcutaneously as directed by your doctor, nurse or pharmacist. See Figure 14.

• Pull the needle out of the skin and press a cotton ball or gauze over the injection site and hold it there for several seconds. Do not recap the needle.

• Dispose of the used syringe and needle as described below. Do not reuse syringes and needles.

2. Intravenous Route:

• Epogen can be injected in your vein through a special access port placed by your healthcare provider. This type of Epogen injection is called an intravenous (IV) injection. This route is usually for hemodialysis patients.

• If you have a dialysis vascular access, make sure it is working by checking it as your healthcare provider has shown you. Be sure to let your healthcare provider know right away if you are having any problems, or if you have any questions.

• Wipe off the venous port of the hemodialysis tubing with an alcohol wipe. See Figure 15.

• Insert the needle of the syringe into the cleaned venous port and push the plunger all the way down to inject all the Epogen. See Figure 16.

• Remove the syringe from the venous port. Do not recap the needle.

• Dispose of the used syringe and needle as described below.

How should I dispose of the vials, syringes, and needles?

Do not reuse the single-dose vials, syringes, or needles. Throw away the vials, syringes, and needles as instructed by your healthcare provider or by following these steps:

• Do not throw the vials, syringes, or needles in the household trash or recycle.

• Do not put the needle cover back on the needle.

• Place all used needles and syringes in a puncture-proof disposable container with a lid. Do not use glass or clear plastic containers, or any container that will be recycled or returned to a store.

• Keep the puncture-proof disposable container out of the reach of children.

• When the puncture-proof disposable container is full, tape around the cap or lid to make sure the cap or lid does not come off. Throw away the puncture-proof disposable container as instructed by your healthcare provider. There may be special state and local laws for disposing of used needles and syringes. Do not throw the puncture-proof disposable container in the household trash. Do not recycle.

Keep Epogen and all medicines out of the reach of children.

These Instructions for Use have been approved by the U.S. Food and Drug Administration.

Manufactured by:

Amgen Inc.
One Amgen Center Drive
Thousand Oaks, CA 91320-1799 U.S.A.

Revised: 12/2024

© 1989-2012, 2024 Amgen Inc. All rights reserved.

1xxxxxx - v4 PMV 3

PACKAGE LABEL

PRINCIPAL DISPLAY PANEL

NDC 55513-126-10
10 x 2000 Units/mL Single Dose Vials
AMGEN®
EPOGEN®
EPOETIN ALFA
recombinant
2000 Units/mL
2000 Units/mL
Single Dose Vials (containing 1 mL)
For Intravenous or Subcutaneous Use Only
Sterile Solution – No Preservative
Store at 2˚ to 8˚C (36˚ to 46˚F). Do Not Freeze or Shake.
Manufactured by Amgen Inc.
Thousand Oaks, CA 91320-1799 U.S.A.
U.S. License No. 1080
©2012,2017 Amgen Inc.
Rx Only

PRINCIPAL DISPLAY PANEL - 2000 Units/mL Vial Package

10 x 2000 Units/mL Single Dose Vials
NDC 55513-126-20

AMGEN

EPOGEN®
EPOETIN ALFA
recombinant

2000
Units/mL
2000 Units/mL
Single Dose Vials (containing 1 mL)
For Intravenous or Subcutaneous Use Only
Sterile Solution - No Preservative
Store at 2° to 8°C (36° to 46°F). Do Not Freeze or Shake.
Manufactured by Amgen Inc.
Thousand Oaks, CA 91320-1799 U.S.A.
U.S. License No. 1080
©2012, 2017, and 2024 Amgen Inc.
Rx Only

PACKAGE LABEL

PRINCIPAL DISPLAY PANEL

NDC 55513-267-10
10 x 3000 Units/mL Single Dose Vials
AMGEN®
EPOGEN®
EPOETIN ALFA
recombinant
3000 Units/mL
3000 Units/mL
Single Dose Vials (containing 1 mL)
For Intravenous or Subcutaneous Use Only
Sterile Solution – No Preservative
Store at 2˚ to 8˚C (36˚ to 46˚F). Do Not Freeze or Shake.
Manufactured by Amgen Inc.
Thousand Oaks, CA 91320-1799 U.S.A.
U.S. License No. 1080
©2012,2017 Amgen Inc.
Rx Only

PRINCIPAL DISPLAY PANEL - 3000 Units/mL Vial Package

10 x 3000 Units/mL Single Dose Vials
NDC 55513-267-20

AMGEN
EPOGEN®
EPOETIN ALFA
recombinant

3000
Units/mL
3000 Units/mL
Single Dose Vials (containing 1 mL)
For Intravenous or Subcutaneous Use Only
Sterile Solution - No Preservative
Store at 2° to 8°C (36° to 46°F). Do Not Freeze or Shake.
Manufactured by Amgen Inc.
Thousand Oaks, CA 91320-1799 U.S.A.
U.S. License No. 1080
©2012, 2017, and 2024 Amgen Inc.
Rx Only

PACKAGE LABEL

PRINCIPAL DISPLAY PANEL

NDC 55513-148-10
10 x 4000 Units/mL Single Dose Vials
AMGEN®
EPOGEN®
EPOETIN ALFA
recombinant
4000 Units/mL
4000 Units/mL
Single Dose Vials (containing 1 mL)
For Intravenous or Subcutaneous Use Only
Sterile Solution – No Preservative
Store at 2˚ to 8˚C (36˚ to 46˚F). Do Not Freeze or Shake.
Manufactured by Amgen Inc.
Thousand Oaks, CA 91320-1799 U.S.A.
U.S. License No. 1080
©2012,2017 Amgen Inc.
Rx Only

PRINCIPAL DISPLAY PANEL - 4000 Units/mL Vial Package

10 x 4000 Units/mL Single Dose Vials
NDC 55513-148-20

AMGEN
EPOGEN®
EPOETIN ALFA
recombinant

4000
Units/mL
4000 Units/mL
Single Dose Vials (containing 1 mL)
For Intravenous or Subcutaneous Use Only
Sterile Solution - No Preservative
Store at 2° to 8°C (36° to 46°F). Do Not Freeze or Shake.
Manufactured by Amgen Inc.
Thousand Oaks, CA 91320-1799 U.S.A.
U.S. License No. 1080
©2012, 2017, and 2024 Amgen Inc.
Rx Only

PACKAGE LABEL

PRINCIPAL DISPLAY PANEL

NDC 55513-144-10
10 x 10,000 Units/mL Single Dose Vials
AMGEN®
EPOGEN®
EPOETIN ALFA
recombinant
10,000 Units/mL
10,000 Units/mL
Single Dose Vials (containing 1 mL)
For Intravenous or Subcutaneous Use Only
Sterile Solution – No Preservative
Store at 2˚ to 8˚C (36˚ to 46˚F). Do Not Freeze or Shake.
Manufactured by Amgen Inc.
Thousand Oaks, CA 91320-1799 U.S.A.
U.S. License No. 1080
©2012,2017 Amgen Inc.
Rx Only

PRINCIPAL DISPLAY PANEL - 10,000 Units/mL Vial Package

10 x 10,000 Units/mL Single Dose Vials
NDC 55513-144-20

AMGEN
EPOGEN®
EPOETIN ALFA
recombinant

10,000
Units/mL
10,000 Units/mL
Single Dose Vials (containing 1 mL)
For Intravenous or Subcutaneous Use Only
Sterile Solution - No Preservative
Store at 2° to 8°C (36° to 46°F). Do Not Freeze or Shake.
Manufactured by Amgen Inc.
Thousand Oaks, CA 91320-1799 U.S.A.
U.S. License No. 1080
©2012, 2017, and 2024 Amgen Inc.
Rx Only

PACKAGE LABEL

PRINCIPAL DISPLAY PANEL

NDC 55513-283-10
AMGEN®
EPOGEN®
EPOETIN ALFA
recombinant
Multiple Dose Vials
20,000 Units/2 mL
(10,000 Units/mL)
20,000 Units/2 mL (10,000 Units/mL)
For Intravenous or Subcutaneous Use Only
Sterile Solution – Preserved
2 mL
Store at 2˚ to 8˚C (36˚ to 46˚F). Do Not Freeze or Shake.
Manufactured by Amgen Inc.
Thousand Oaks, CA 91320-1799 U.S.A.
U.S. License No. 1080
©2012,2017 Amgen Inc.
Rx Only

PRINCIPAL DISPLAY PANEL - 2 mL Vial Package

10 x 2 mL Multiple Dose Vials 20,000 Units/2 mL (10,000 Units/mL)
NDC 55513-283-20
AMGEN
EPOGEN®
EPOETIN ALFA
recombinant
20,000 Units / 2 mL
(10,000 Units / mL)
20,000 Units / 2 mL (10,000 Units / mL)
Multiple Dose Vials
For Intravenous or Subcutaneous Use Only
Sterile Solution - Preserved
2 mL
Store at 2° to 8°C (36° to 46°F). Do Not Freeze or Shake.
Manufactured by Amgen Inc.
Thousand Oaks, CA 91320-1799 U.S.A.
U.S. License No. 1080
©2012, 2017, and 2024 Amgen Inc.
Rx Only

PACKAGE LABEL

PRINCIPAL DISPLAY PANEL

NDC 55513-478-10
AMGEN®
EPOGEN®
EPOETIN ALFA
recombinant
Multiple Dose Vials
20,000 Units/mL
20,000 Units/mL
1 mL
For Intravenous or Subcutaneous Use Only
Sterile Solution – Preserved
Store at 2˚ to 8˚C (36˚ to 46˚F). Do Not Freeze or Shake.
Manufactured by Amgen Inc.
Thousand Oaks, CA 91320-1799 U.S.A.
U.S. License No. 1080
©2012,2017 Amgen Inc.
Rx Only

PRINCIPAL DISPLAY PANEL - 1 mL Vial Package

10 x 20,000 Units/mL Multiple Dose Vials
NDC 55513-478-20
AMGEN
EPOGEN®
EPOETIN ALFA
recombinant
20,000
Units / mL
20,000 Units / mL
Multiple Dose Vials
1 mL
For Intravenous or Subcutaneous Use Only
Sterile Solution - Preserved
Store at 2° to 8°C (36° to 46°F). Do Not Freeze or Shake.
Manufactured by Amgen Inc.
Thousand Oaks, CA 91320-1799 U.S.A.
U.S. License No. 1080
©2012, 2017, and 2024 Amgen Inc.
Rx Only